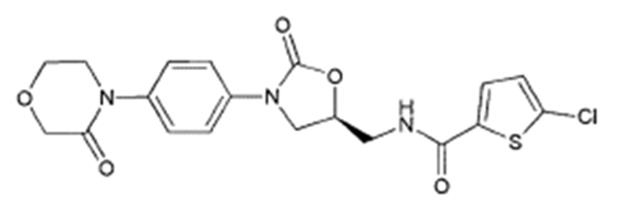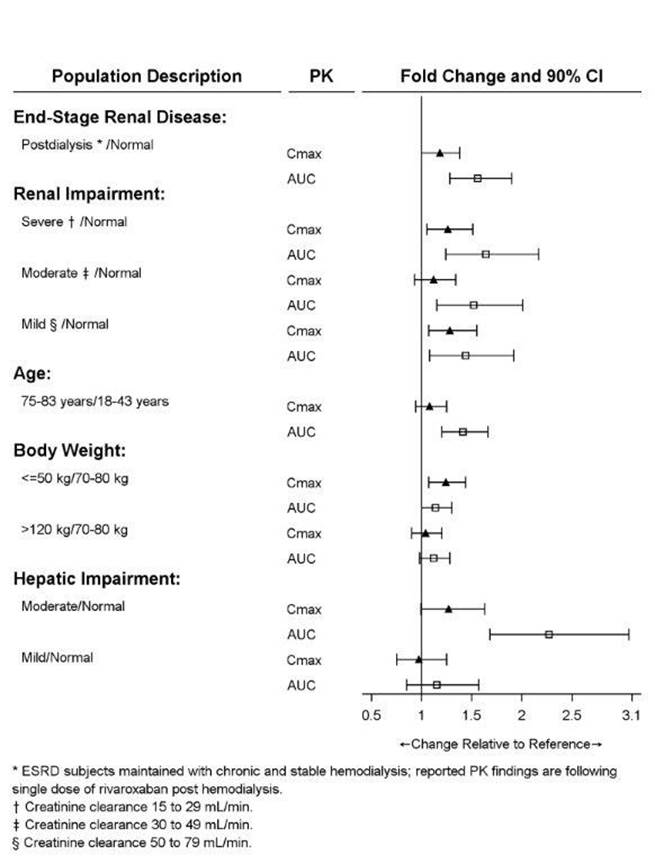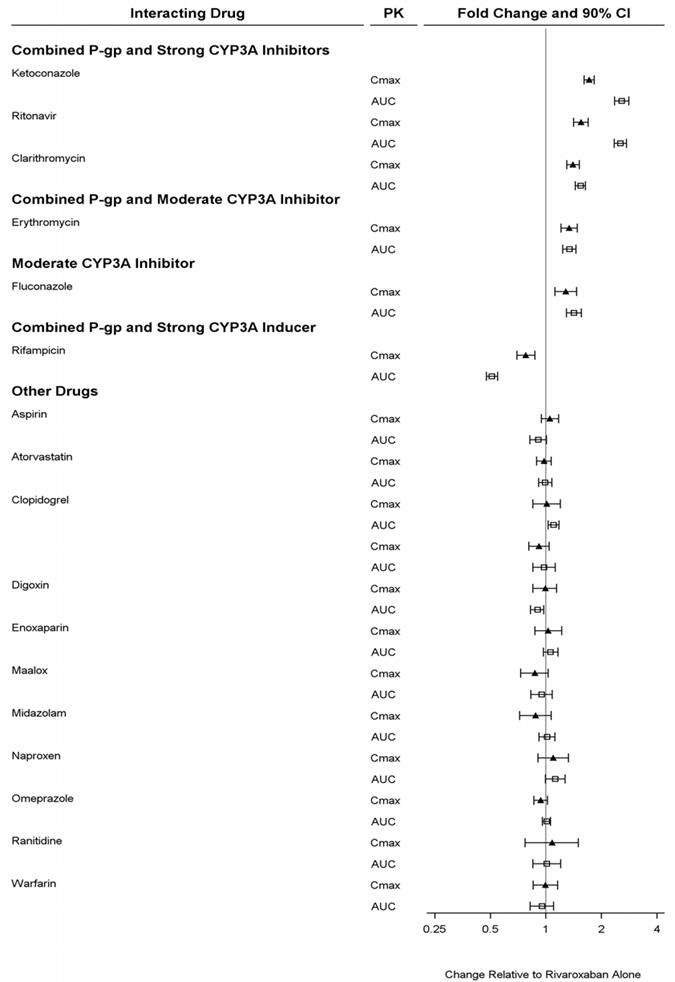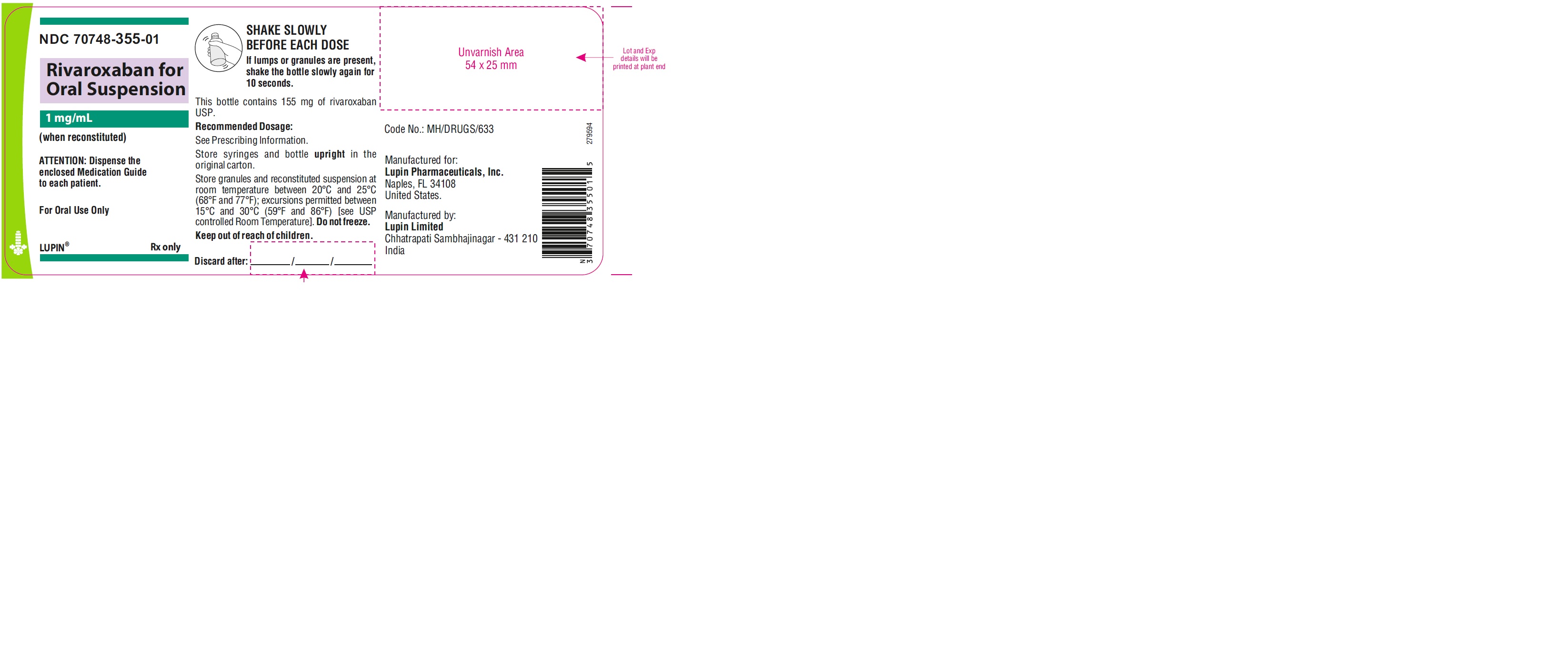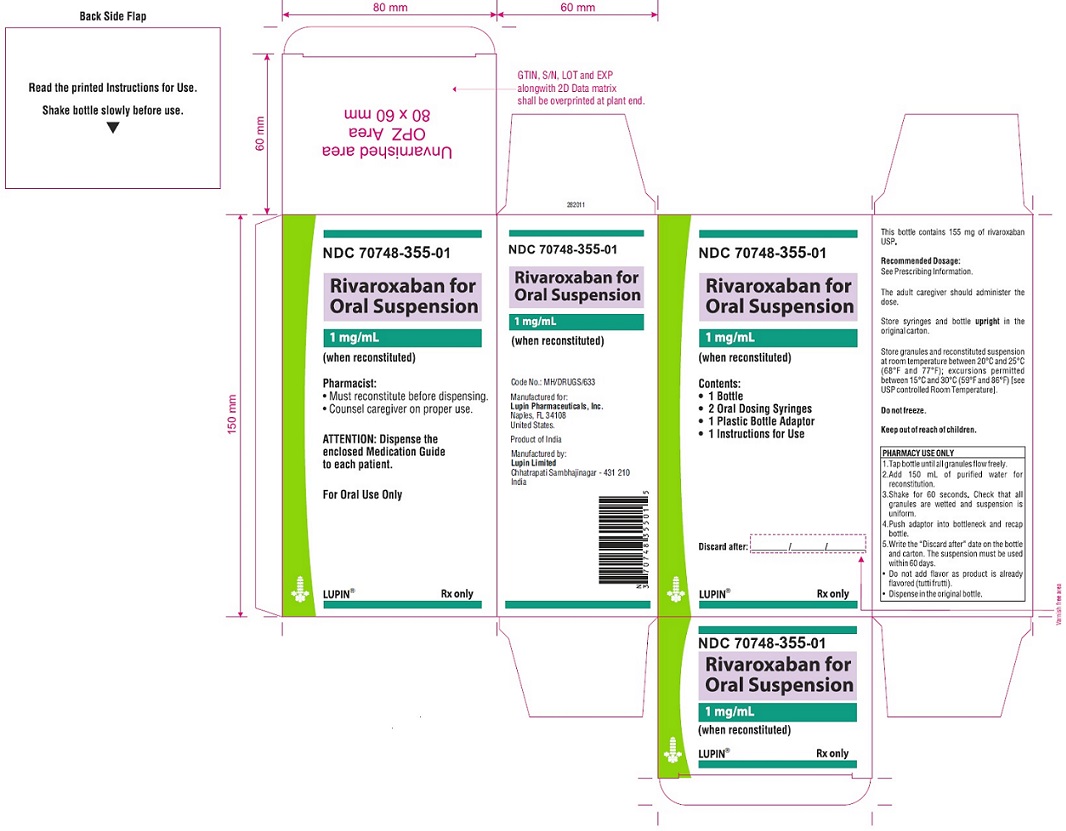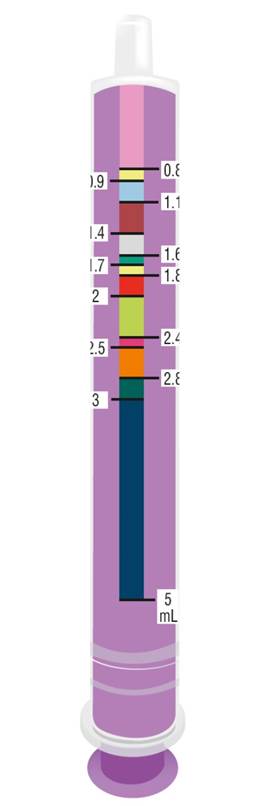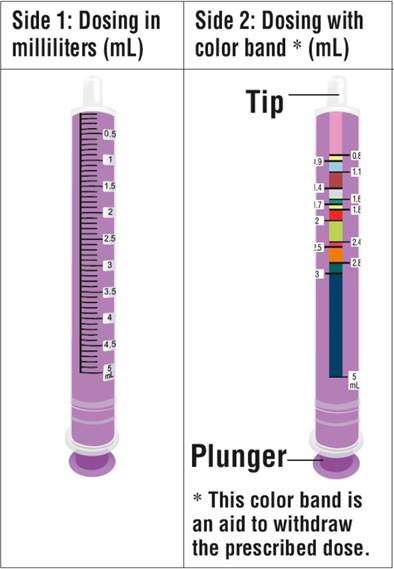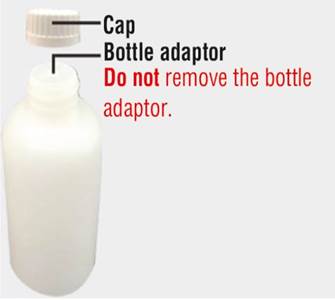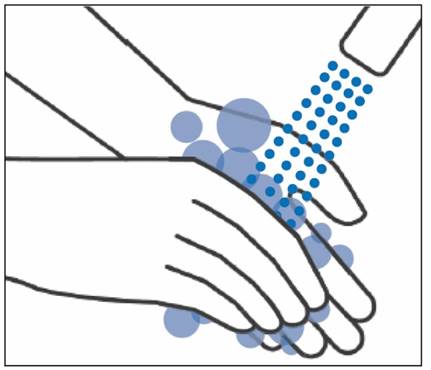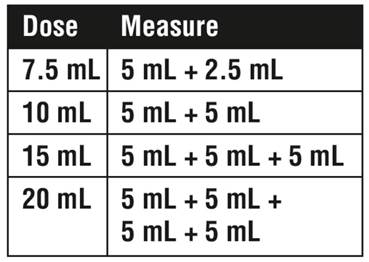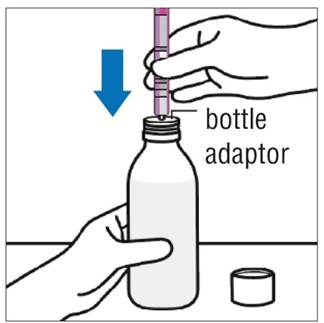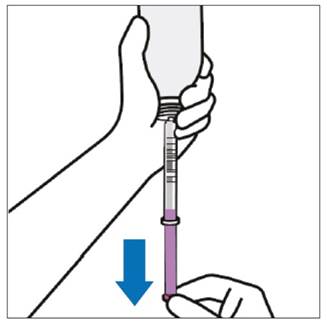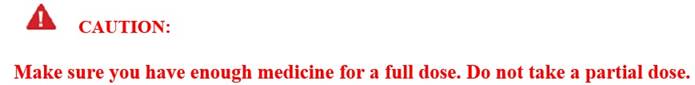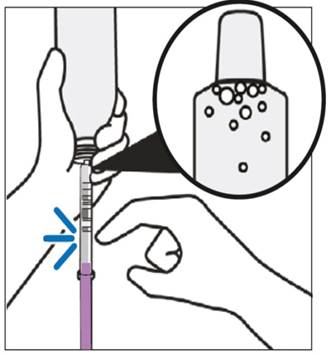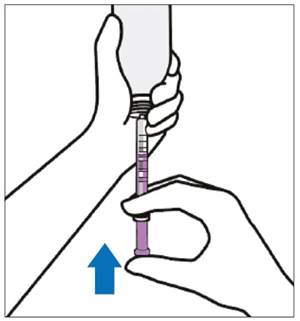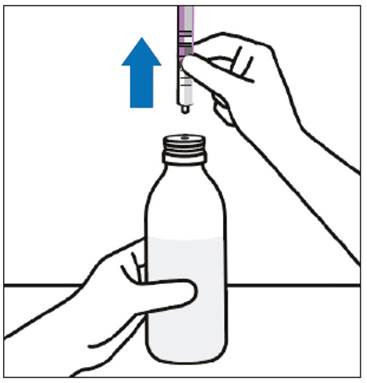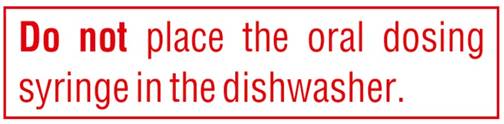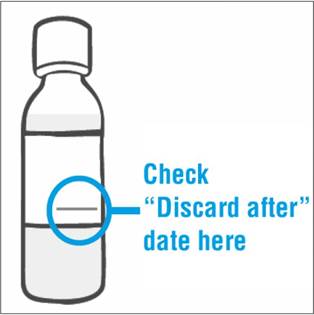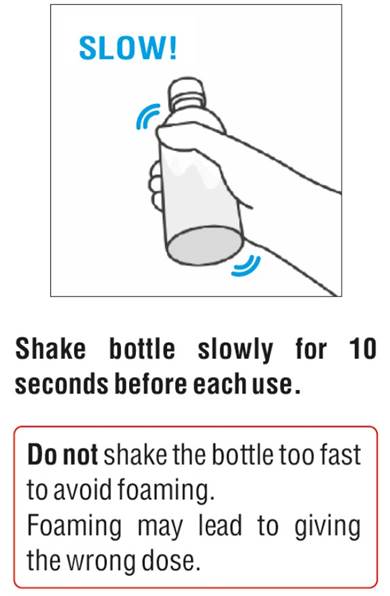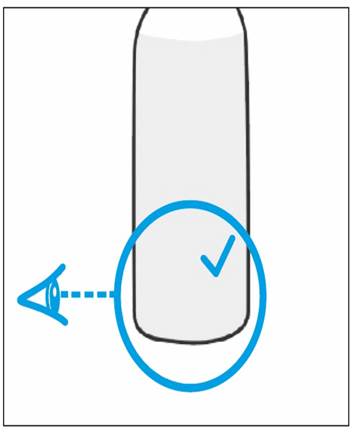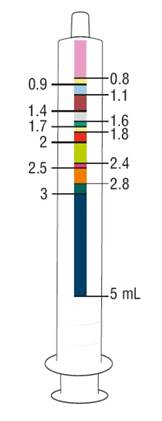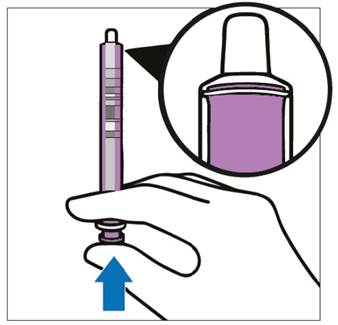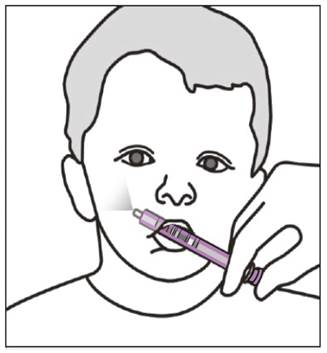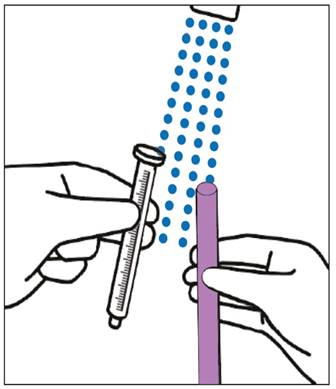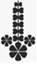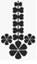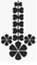 DRUG LABEL: rivaroxaban granule
NDC: 70748-355 | Form: FOR SUSPENSION
Manufacturer: Lupin Pharmaceuticals, Inc.
Category: prescription | Type: HUMAN PRESCRIPTION DRUG LABEL
Date: 20251110

ACTIVE INGREDIENTS: RIVAROXABAN 155 mg/1 1
INACTIVE INGREDIENTS: ANHYDROUS CITRIC ACID; CARBOXYMETHYLCELLULOSE SODIUM, UNSPECIFIED; MANNITOL; MICROCRYSTALLINE CELLULOSE; SODIUM BENZOATE; SUCRALOSE; XANTHAN GUM; HYPROMELLOSE, UNSPECIFIED

HIGHLIGHTS OF PRESCRIBING INFORMATION

These highlights do not include all the information needed to use
RIVAROXABAN FOR ORAL SUSPENSION safely and effectively. See full prescribing information for RIVAROXABAN FOR ORAL SUSPENSION.
RIVAROXABAN for oral suspension
Initial U.S. Approval: 2011

RECENT MAJOR CHANGES

Warnings and Precautions (5.2) 06/2025

WARNING: (A) PREMATURE DISCONTINUATION OF RIVAROXABAN FOR ORAL SUSPENSION INCREASES THE RISK OF THROMBOTIC EVENTS, (B) SPINAL/EPIDURAL HEMATOMA

WARNING: (A) PREMATURE DISCONTINUATION OF RIVAROXABAN FOR ORAL SUSPENSION INCREASES THE RISK OF THROMBOTIC EVENTS,

(B) SPINAL/EPIDURAL HEMATOMA

See full prescribing information for complete boxed warning.

(A) Premature discontinuation of rivaroxaban for oral suspension increases the risk of thrombotic events

Premature discontinuation of any oral anticoagulant, including rivaroxaban for oral suspension, increases the risk of thrombotic events. To reduce this risk, consider coverage with another anticoagulant if rivaroxaban for oral suspension is discontinued for a reason other than pathological bleeding or completion of a course of therapy. (2.2, 2.3, 5.1).

(B) Spinal/epidural hematoma

Epidural or spinal hematomas have occurred in patients treated with rivaroxaban for oral suspension who are receiving neuraxial anesthesia or undergoing spinal puncture. These hematomas may result in long-term or permanent paralysis. (5.2, 5.3, 6.2)

Monitor patients frequently for signs and symptoms of neurological impairment and if observed, treat urgently. Consider the benefits and risks before neuraxial intervention in patients who are or who need to be anticoagulated. (5.3)

1 INDICATIONS AND USAGE

Rivaroxaban for oral suspension is a factor Xa inhibitor indicated:

- for treatment of VTE and reduction in the risk of recurrent VTE in pediatric patients from birth to less than 18 years (1.9)
- for thromboprophylaxis in pediatric patients 2 years and older with congenital heart disease after the Fontan procedure (1.10)

2 DOSAGE AND ADMINISTRATION

- Pediatric Patients: See dosing recommendations in the Full Prescribing Information (2.2)

3 DOSAGE FORMS AND STRENGTHS

- For Oral Suspension: 1 mg/mL once reconstituted (3)

4 CONTRAINDICATIONS

- Active pathological bleeding (4)
- Severe hypersensitivity reaction to rivaroxaban for oral suspension (4)

5 WARNINGS AND PRECAUTIONS

- Risk of Bleeding: Rivaroxaban for oral suspension can cause serious and fatal bleeding. An agent to reverse the activity of rivaroxaban is available. (5.2)
- Pregnancy-Related Hemorrhage: Use rivaroxaban for oral suspension with caution in pregnant women due to the potential for obstetric hemorrhage and/or emergent delivery. (5.7, 8.1)
- Prosthetic Heart Valves: Rivaroxaban for oral suspension use not recommended. (5.8)
- Increased Risk of Thrombosis in Patients with Triple Positive Antiphospholipid Syndrome: Rivaroxaban for oral suspension use not recommended. (5.10)

6 ADVERSE REACTIONS

- The most common adverse reactions (>10 %) in pediatric patients were bleeding, cough, vomiting, and gastroenteritis. (6.1)

To report SUSPECTED ADVERSE REACTIONS, contact Lupin Pharmaceuticals, Inc. at 1-800-399-2561, or FDA at 1-800-FDA-1088 or www.fda.gov/medwatch.

7 DRUG INTERACTIONS

- Avoid combined P-gp and strong CYP3A inhibitors and inducers (7.2, 7.3)
- Anticoagulants: Avoid concomitant use (7.4)

8 USE IN SPECIFIC POPULATIONS

- Renal Impairment: Avoid or adjust dose (8.6)
- Hepatic Impairment: Avoid use in Child-Pugh B and C hepatic impairment or hepatic disease associated with coagulopathy (8.7)

FULL PRESCRIBING INFORMATION

WARNING: (A) PREMATURE DISCONTINUATION OF RIVAROXABAN FOR ORAL SUSPENSION INCREASES THE RISK OF THROMBOTIC EVENTS, (B) SPINAL/EPIDURAL HEMATOMA

A. Premature discontinuation of rivaroxaban for oral suspension increases the risk of thrombotic events

Premature discontinuation of any oral anticoagulant, including rivaroxaban for oral suspension, increases the risk of thrombotic events. If anticoagulation with rivaroxaban for oral suspension is discontinued for a reason other than pathological bleeding or completion of a course of therapy, consider coverage with another anticoagulant [see Dosage and Administration (2.3, 2.4) and Warnings and Precautions (5.1).

B. Spinal/epidural hematoma

Epidural or spinal hematomas have occurred in patients treated with rivaroxaban for oral suspension who are receiving neuraxial anesthesia or undergoing spinal puncture. These hematomas may result in long-term or permanent paralysis. Consider these risks when scheduling patients for spinal procedures. Factors that can increase the risk of developing epidural or spinal hematomas in these patients include:

- use of indwelling epidural catheters
- concomitant use of other drugs that affect hemostasis, such as non-
- steroidal anti-inflammatory drugs (NSAIDs), platelet inhibitors, other anticoagulants
- a history of traumatic or repeated epidural or spinal punctures
- a history of spinal deformity or spinal surgery
- optimal timing between the administration of rivaroxaban for oral suspension and neuraxial procedures is not known [see Warnings and Precautions (5.2, 5.3) and Adverse Reactions (6.2)].

Monitor patients frequently for signs and symptoms of neurological impairment. If neurological compromise is noted, urgent treatment is necessary [see Warnings and Precautions (5.3)].

Consider the benefits and risks before neuraxial intervention in patients anticoagulated or to be anticoagulated for thromboprophylaxis [see Warnings and Precautions (5.3)].

1 INDICATIONS AND USAGE

1.9 Treatment of Venous Thromboembolism and Reduction in Risk of Recurrent Venous Thromboembolism in Pediatric Patients

Rivaroxaban for oral suspension is indicated for the treatment of venous thromboembolism (VTE) and the reduction in the risk of recurrent VTE in pediatric patients from birth to less than 18 years after at least 5 days of initial parenteral anticoagulant treatment.

1.10 Thromboprophylaxis in Pediatric Patients with Congenital Heart Disease after the Fontan Procedure

Rivaroxaban for oral suspension is indicated for thromboprophylaxis in pediatric patients aged 2 years and older with congenital heart disease who have undergone the Fontan procedure.

2 DOSAGE AND ADMINISTRATION

2.2 Recommended Dosage in Pediatric Patients

Treatment of Venous Thromboembolism and Reduction in Risk of Recurrent Venous Thromboembolism in Pediatric Patients

Table 2: Recommended Dosage in Pediatric Patients Birth to Less than 18 Years for Treatment of and Reduction in Risk of Recurrent VTE*,†
Dosage Form | Body Weight | 1 mg Rivaroxaban for Oral Suspension = 1 mL Suspension
Dosage Form | Body Weight | Dosage |  |  | Total Daily Dose‡
Dosage Form | Body Weight | Once a Day§ | 2 Times a Day§ | 3 Times a Day§
Oral Suspension Only | 2.6 kg to 2.9 kg |  |  | 0.8 mg | 2.4 mg
Oral Suspension Only | 3 kg to 3.9 kg |  |  | 0.9 mg | 2.7 mg
Oral Suspension Only | 4 kg to 4.9 kg |  |  | 1.4 mg | 4.2 mg
Oral Suspension Only | 5 kg to 6.9 kg |  |  | 1.6 mg | 4.8 mg
Oral Suspension Only | 7 kg to 7.9 kg |  |  | 1.8 mg | 5.4 mg
Oral Suspension Only | 8 kg to 8.9 kg |  |  | 2.4 mg | 7.2 mg
Oral Suspension Only | 9 kg to 9.9 kg |  |  | 2.8 mg | 8.4 mg
Oral Suspension Only | 10 kg to 11.9 kg |  |  | 3 mg | 9 mg
Oral Suspension Only | 12 kg to 29.9 kg |  | 5 mg |  | 10 mg
Oral Suspension | 30 kg to 49.9 kg | 15 mg |  |  | 15 mg
Oral Suspension | ≥50 kg | 20 mg |  |  | 20 mg

* Initiate rivaroxaban for oral suspension treatment following at least 5 days of initial parenteral anticoagulation therapy.

† Patients <6 months of age should meet the following criteria: at birth were at least 37 weeks of gestation, have had at least 10 days of oral feeding, and weigh ≥2.6 kg at the time of dosing.

‡ All doses should be taken with feeding or with food since exposures match that of 20 mg daily dose in adults.

§ Once a day: approximately 24 hours apart; 2 times a day: approximately 12 hours apart; 3 times a day: approximately 8 hours apart

Dosing of rivaroxaban for oral suspension was not studied and therefore dosing cannot be reliably determined in the following patient populations. Its use is therefore not recommended in children less than 6 months of age with any of the following:

- Less than 37 weeks of gestation at birth
- Less than 10 days of oral feeding
- Body weight of less than 2.6 kg.

To increase absorption, all doses should be taken with feeding or with food.

Monitor the child's weight and review the dose regularly, especially for children below 12 kg. This is to ensure a therapeutic dose is maintained.

All Pediatric Patients (except <2 years old with catheter-related thrombosis): Therapy with rivaroxaban for oral suspension should be continued for at least 3 months in children with thrombosis. Treatment can be extended up to 12 months when clinically necessary. The benefit of continued therapy beyond 3 months should be assessed on an individual basis taking into account the risk for recurrent thrombosis versus the potential risk of bleeding.

Pediatric Patients <2 Years Old with Catheter-Related Thrombosis: Therapy with rivaroxaban for oral suspension should be continued for at least 1 month in children less than 2 years old with catheter-related thrombosis. Treatment can be extended up to 3 months when clinically necessary. The benefit of continued therapy beyond 1 month should be assessed on an individual basis taking into account the risk for recurrent thrombosis versus the potential risk of bleeding.

Thromboprophylaxis in Pediatric Patients with Congenital Heart Disease after the Fontan Procedure

Table 3: Recommended Dosage for Thromboprophylaxis in Pediatric Patients with Congenital Heart Disease
Dosage Form | Body Weight | 1 mg Rivaroxaban for Oral Suspension = 1 mL Suspension
Dosage Form | Body Weight | Dosage |  | Total Daily Dose*
Dosage Form | Body Weight | Once a Day† | 2 Times a Day†
Oral Suspension Only | 7 kg to 7.9 kg |  | 1.1 mg | 2.2 mg
Oral Suspension Only | 8 kg to 9.9 kg |  | 1.6 mg | 3.2 mg
Oral Suspension Only | 10 kg to 11.9 kg |  | 1.7 mg | 3.4 mg
Oral Suspension Only | 12 kg to 19.9 kg |  | 2 mg | 4 mg
Oral Suspension Only | 20 kg to 29.9 kg |  | 2.5 mg | 5 mg
Oral Suspension Only | 30 kg to 49.9 kg | 7.5 mg |  | 7.5 mg
Oral Suspension | ≥50 kg | 10 mg |  | 10 mg
* All doses can be taken with or without food since exposures match that of 10 mg daily dose in adults.
† Once a day: approximately 24 hours apart; 2 times a day: approximately 12 hours apart.

Administration in Pediatric Patients

Food Effect:

For the treatment of VTE in children, the dose should be taken with food to increase absorption. For thromboprophylaxis after Fontan procedure, the dose can be taken with or without food.

Vomit or Spit Up:

If the patient vomits or spits up the dose within 30 minutes after receiving the dose, a new dose should be given. However, if the patient vomits more than 30 minutes after the dose is taken, the dose should not be re-administered and the next dose should be taken as scheduled. If the patient vomits or spits up the dose repeatedly, the caregiver should contact the child's doctor right away.

For children unable to swallow 10, 15, or 20 mg whole tablets, rivaroxaban for oral suspension should be used.

Use in Renal Impairment in Pediatric Patients

Patients 1 Year of Age or Older:

- Mild renal impairment (eGFR: 50 to ≤ 80 mL/min/1.73 m^2): No dose adjustment is required.
- Moderate or severe renal impairment (eGFR: <50 mL/min/1.73 m^2): avoid use, as limited clinical data are available.

Estimated glomerular filtration rate (eGFR) can be done using the updated Schwartz formula, eGFR (Schwartz) = (0.413 x height in cm)/serum creatinine in mg/dL, if serum creatinine (SCr) is measured by an enzymatic creatinine method that has been calibrated to be traceable to isotope dilution mass spectrometry (IDMS).

If SCr is measured with routine methods that have not been recalibrated to be traceable to IDMS (e.g., the traditional Jaff¡SR reaction), the eGFR should be obtained from the original Schwartz formula: eGFR (mL/min/1.73 m^2) = k* height (cm)/SCr (mg/dL), where k is proportionality constant:

k = 0.55 in children 1 year to 13 years

k = 0.55 in girls > 13 and < 18 years

k = 0.70 in boys > 13 and < 18 years

Patients Less than 1 Year of Age:

Determine renal function using serum creatinine. Avoid use of rivaroxaban for oral suspension in pediatric patients younger than 1 year with serum creatinine results above 97.5th percentile, as no clinical data are available.

Table 4: Reference Values of Serum Creatinine in Pediatric Patients <1 Year of Age
Age | 97.5 th Percentile of Creatinine (mg/dL) | 97.5 th Percentile of Creatinine (µmol/L)
Week 2 | 0.52 | 46
Week 3 | 0.46 | 41
Week 4 | 0.42 | 37
Month 2 | 0.37 | 33
Month 3 | 0.34 | 30
Month 4 to 6 | 0.34 | 30
Month 7 to 9 | 0.34 | 30
Month 10 to 12 | 0.36 | 32

2.3 Switching to and from Rivaroxaban for Oral Suspension

Switching from Warfarin to Rivaroxaban for Oral Suspension

When switching patients from warfarin to rivaroxaban for oral suspension, discontinue warfarin and start rivaroxaban for oral suspension as soon as the International Normalized Ratio (INR) is below 2.5 in pediatric patients to avoid periods of inadequate anticoagulation.

Switching from Rivaroxaban for Oral Suspension to Warfarin

- Pediatric Patients:

To ensure adequate anticoagulation during the transition from rivaroxaban for oral suspension to warfarin, continue rivaroxaban for oral suspension for at least 2 days after the first dose of warfarin. After 2 days of co-administration, an INR should be obtained prior to the next scheduled dose of rivaroxaban for oral suspension. Co-administration of rivaroxaban for oral suspension and warfarin is advised to continue until the INR is ≥ 2.

Once rivaroxaban for oral suspension is discontinued, INR testing may be done reliably 24 hours after the last dose.

Switching from Rivaroxaban for Oral Suspension to Anticoagulants other than Warfarin

For pediatric patients currently taking rivaroxaban for oral suspension and transitioning to an anticoagulant with rapid onset, discontinue rivaroxaban for oral suspension and give the first dose of the other anticoagulant (oral or parenteral) at the time that the next rivaroxaban for oral suspension dose would have been taken [see Drug Interactions (7.4)].

Switching from Anticoagulants other than Warfarin to Rivaroxaban for Oral Suspension

For pediatric patients currently receiving an anticoagulant other than warfarin, start rivaroxaban for oral suspension 0 to 2 hours prior to the next scheduled administration of the drug (e.g., low molecular weight heparin or non- warfarin oral anticoagulant) and omit administration of the other anticoagulant. For unfractionated heparin being administered by continuous infusion, stop the infusion and start rivaroxaban for oral suspension at the same time.

2.4 Discontinuation for Surgery and other Interventions

If anticoagulation must be discontinued to reduce the risk of bleeding with surgical or other procedures, rivaroxaban for oral suspension should be stopped at least 24 hours before the procedure to reduce the risk of bleeding [see Warnings and Precautions (5.2)]. In deciding whether a procedure should be delayed until 24 hours after the last dose of rivaroxaban for oral suspension, the increased risk of bleeding should be weighed against the urgency of intervention. Rivaroxaban for oral suspension should be restarted after the surgical or other procedures as soon as adequate hemostasis has been established, noting that the time to onset of therapeutic effect is short [see Warnings and Precautions (5.1)]. If oral medication cannot be taken during or after surgical intervention, consider administering a parenteral anticoagulant.

2.5 Missed Dose

Pediatric Patients

- If rivaroxaban for oral suspension is taken once a day, the patient should take the missed dose as soon as possible once it is noticed, but only on the same day. If this is not possible, the patient should skip the dose and continue with the next dose as prescribed. The patient should not take two doses to make up for a missed dose.
- If rivaroxaban for oral suspension is taken two times a day, the patient should take the missed morning dose as soon as possible once it is noticed. A missed morning dose may be taken together with the evening dose. A missed evening dose can only be taken in the same evening.
- If rivaroxaban for oral suspension is taken three times a day, if a dose is missed, the patient should skip the missed dose and go back to the regular dosing schedule at the usual time without compensating for the missed dose.

On the following day, the patient should continue with their regular regimen.

2.6 Administration Options

Administration of Rivaroxaban for Oral Suspension via NG Tube or Gastric Feeding Tube Rivaroxaban for oral suspension may be given through NG or gastric feeding tube. After the administration, flush the feeding tube with water.

For the treatment or reduction in risk of recurrent VTE in pediatric patients, the dose should then be immediately followed by enteral feeding to increase absorption. For the thromboprophylaxis in pediatric patients with congenital heart disease who have undergone the Fontan procedure, the dose does not require to be followed by enteral feeding.

An in vitro compatibility study indicated that rivaroxaban for oral suspension can be used with PVC, polyurethane or silicone NG tubing.

2.7 Preparation Instructions for Pharmacy of Rivaroxaban for Oral Suspension

Do not add flavor as product is already flavored (tutti frutti).

Reconstitute before dispensing:

- Tap the bottle until all granules flow freely.
- Add 150 mL of purified water for reconstitution.
- Shake for 60 seconds. Check that all granules are wetted and the suspension is uniform.
- Push the adaptor into bottleneck and recap bottle.
- The suspension must be used within 60 days.
- Write the "Discard after" date on the bottle and carton.

Dispensing Instructions:

- Dispense in the original bottle.
- Dispense the bottle upright with the syringes provided in the original carton.

Store reconstituted suspension at room temperature between 20°C and 25°C (68°F and 77°F); excursions permitted between 15°C and 30°C (59°F and 86°F). Do not freeze.

It is recommended the pharmacist counsel the caregiver on proper use. Alert the patient or caregiver to read the Medication Guide and Instructions for Use.

3 DOSAGE FORMS AND STRENGTHS

For oral suspension: white to off-white granules; once reconstituted, provide white to off-white flavored opaque liquid with a concentration of 1 mg/mL.

4 CONTRAINDICATIONS

Rivaroxaban for oral suspension is contraindicated in patients with:

- active pathological bleeding [see Warnings and Precautions (5.2)]
- severe hypersensitivity reaction to rivaroxaban for oral suspension (e.g., anaphylactic reactions) [see Adverse Reactions (6.2)]

5 WARNINGS AND PRECAUTIONS

5.1 Increased Risk of Thrombotic Events after Premature Discontinuation

Premature discontinuation of any oral anticoagulant, including rivaroxaban for oral suspension, in the absence of adequate alternative anticoagulation increases the risk of thrombotic events. An increased rate of stroke was observed during the transition from rivaroxaban tablets to warfarin in clinical trials in another indication in patients. If rivaroxaban for oral suspension is discontinued for a reason other than pathological bleeding or completion of a course of therapy, consider coverage with another anticoagulant [see Dosage and Administration (2.3, 2.4)].

5.2 Risk of Bleeding

Rivaroxaban for oral suspension increases the risk of bleeding, including in any organ, and can cause serious or fatal bleeding. In deciding whether to prescribe rivaroxaban for oral suspension to patients at increased risk of bleeding, the risk of thrombotic events should be weighed against the risk of bleeding.

Promptly evaluate any signs or symptoms of blood loss and consider the need for blood replacement. Discontinue rivaroxaban for oral suspension in patients with active pathological hemorrhage. The terminal elimination half-life of rivaroxaban is 5 to 9 hours in healthy subjects aged 20 to 45 years.

Concomitant use of other drugs that impair hemostasis increases the risk of bleeding. These include aspirin, P2Y12 platelet inhibitors, dual antiplatelet therapy, other antithrombotic agents, fibrinolytic therapy, non-steroidal anti-inflammatory drugs (NSAIDs) [see Drug Interactions (7.4)], selective serotonin reuptake inhibitors, and serotonin norepinephrine reuptake inhibitors.

Concomitant use of drugs that are known combined P-gp and strong CYP3A inhibitors increases rivaroxaban exposure and may increase bleeding risk [see Drug Interactions (7.2)].

Risk of Hemorrhage in Acutely Ill Medical Patients at High Risk of Bleeding

Acutely ill medical patients with the following conditions are at increased risk of bleeding with the use of rivaroxaban for oral suspension for primary VTE prophylaxis: history of bronchiectasis, pulmonary cavitation, or pulmonary hemorrhage, active cancer (i.e., undergoing acute, in-hospital cancer treatment), active gastroduodenal ulcer in the three months prior to treatment, history of bleeding in the three months prior to treatment, or dual antiplatelet therapy. rivaroxaban for oral suspension is not for use for primary VTE prophylaxis in these hospitalized, acutely ill medical patients at high risk of bleeding.

Reversal of Anticoagulant Effect

An agent to reverse the anti-factor Xa activity of rivaroxaban is available. Because of high plasma protein binding, rivaroxaban is not dialyzable [see Clinical Pharmacology (12.3)]. Protamine sulfate and vitamin K are not expected to affect the anticoagulant activity of rivaroxaban. Use of procoagulant reversal agents, such as prothrombin complex concentrate (PCC), activated prothrombin complex concentrate or recombinant factor VIIa, may be considered but has not been evaluated in clinical efficacy and safety studies. Monitoring for the anticoagulation effect of rivaroxaban using a clotting test (PT, INR or aPTT) or anti-factor Xa (FXa) activity is not recommended.

5.3 Spinal/Epidural Anesthesia or Puncture

When neuraxial anesthesia (spinal/epidural anesthesia) or spinal puncture is employed, patients treated with anticoagulant agents for prevention of thromboembolic complications are at risk of developing an epidural or spinal hematoma which can result in long-term or permanent paralysis [see Boxed Warning].

To reduce the potential risk of bleeding associated with the concurrent use of rivaroxaban for oral suspension and epidural or spinal anesthesia/analgesia or spinal puncture, consider the pharmacokinetic profile of rivaroxaban for oral suspension [see Clinical Pharmacology (12.3)]. Placement or removal of an epidural catheter or lumbar puncture is best performed when the anticoagulant effect of rivaroxaban for oral suspension is low; however, the exact timing to reach a sufficiently low anticoagulant effect in each patient is not known.

An indwelling epidural or intrathecal catheter should not be removed before at least 2 half-lives have elapsed (i.e., 18 hours in young patients aged 20 to 45 years and 26 hours in elderly patients aged 60 to 76 years), after the last administration of rivaroxaban for oral suspension [see Clinical Pharmacology (12.3)]. The next rivaroxaban for oral suspension dose should not be administered earlier than 6 hours after the removal of the catheter. If traumatic puncture occurs, delay the administration of rivaroxaban for oral suspension for 24 hours.

Should the physician decide to administer anticoagulation in the context of epidural or spinal anesthesia/analgesia or lumbar puncture, monitor frequently to detect any signs or symptoms of neurological impairment, such as midline back pain, sensory and motor deficits (numbness, tingling, or weakness in lower limbs), bowel and/or bladder dysfunction. Instruct patients to immediately report if they experience any of the above signs or symptoms. If signs or symptoms of spinal hematoma are suspected, initiate urgent diagnosis and treatment including consideration for spinal cord decompression even though such treatment may not prevent or reverse neurological sequelae.

5.4 Use in Patients with Renal Impairment

Pediatric Patients

There are limited clinical data in pediatric patients 1 year or older with moderate or severe renal impairment (eGFR <50 mL/min/1.73 m^2); therefore, avoid the use of rivaroxaban for oral suspension in these patients.

There are no clinical data in pediatric patients younger than 1 year with serum creatinine results above 97.5thpercentile; therefore, avoid the use of rivaroxaban for oral suspension in these patients [see Dosage and Administration (2.2) and Use in Specific Populations (8.6)].

5.5 Use in Patients with Hepatic Impairment

No clinical data are available for adult patients with severe hepatic impairment.

Avoid use of rivaroxaban for oral suspension in patients with moderate (Child-Pugh B) and severe (Child-Pugh C) hepatic impairment or with any hepatic disease associated with coagulopathy since drug exposure and bleeding risk may be increased [see Use in Specific Populations (8.7)].

No clinical data are available in pediatric patients with hepatic impairment.

5.6 Use with P-gp and Strong CYP3A Inhibitors or Inducers

Avoid concomitant use of rivaroxaban for oral suspension with known combined P-gp and strong CYP3A inhibitors [see Drug Interactions (7.2)].

Avoid concomitant use of rivaroxaban for oral suspension with drugs that are known combined P-gp and strong CYP3A inducers [see Drug Interactions (7.3)].

5.7 Risk of Pregnancy-Related Hemorrhage

In pregnant women, rivaroxaban for oral suspension should be used only if the potential benefit justifies the potential risk to the mother and fetus. Rivaroxaban for oral suspension dosing in pregnancy has not been studied. The anticoagulant effect of rivaroxaban for oral suspension cannot be monitored with standard laboratory testing. Promptly evaluate any signs or symptoms suggesting blood loss (e.g., a drop in hemoglobin and/or hematocrit, hypotension, or fetal distress) [see Warnings and Precautions (5.2) and Use in Specific Populations (8.1)].

5.8 Patients with Prosthetic Heart Valves

On the basis of the GALILEO study, use of rivaroxaban tablets is not recommended in patients who have had transcatheter aortic valve replacement (TAVR) because patients randomized to rivaroxaban tablets experienced higher rates of death and bleeding compared to those randomized to an anti-platelet regimen. The safety and efficacy of rivaroxaban for oral suspension have not been studied in patients with other prosthetic heart valves or other valve procedures. Use of rivaroxaban for oral suspension is not recommended in patients with prosthetic heart valves.

5.9 Acute PE in Hemodynamically Unstable Patients or Patients Who Require Thrombolysis or Pulmonary Embolectomy

Initiation of rivaroxaban for oral suspension is not recommended acutely as an alternative to unfractionated heparin in patients with pulmonary embolism who present with hemodynamic instability or who may receive thrombolysis or pulmonary embolectomy.

5.10 Increased Risk of Thrombosis in Patients with Triple Positive Antiphospholipid Syndrome

Direct-acting oral anticoagulants (DOACs), including rivaroxaban for oral suspension, are not recommended for use in patients with triple-positive antiphospholipid syndrome (APS). For patients with APS (especially those who are triple positive [positive for lupus anticoagulant, anticardiolipin, and anti-beta 2-glycoprotein I antibodies]), treatment with DOACs has been associated with increased rates of recurrent thrombotic events compared with vitamin K antagonist therapy.

6 ADVERSE REACTIONS

The following clinically significant adverse reactions are also discussed in other sections of the labeling:

- Increased Risk of Stroke After Discontinuation in Another Indication [see Boxed Warning and Warnings and Precautions (5.1)]
- Bleeding Risk [see Warnings and Precautions (5.2, 5.4, 5.5, 5.6, 5.7)]
- Spinal/Epidural Hematoma [see Boxed Warning and Warnings and Precautions (5.3)]

6.1 Clinical Trials Experience

Because clinical trials are conducted under widely varying conditions, adverse reaction rates observed in the clinical trials of a drug cannot be directly compared to rates in the clinical trials of another drug and may not reflect the rates observed in clinical practice.

Pediatric Patients

Treatment of Venous Thromboembolism and Reduction in Risk of Recurrent Venous Thromboembolism in Pediatric Patients:

The safety assessment is based on data from the EINSTEIN Junior Phase 3 study in 491 patients from birth to less than 18 years of age. Patients were randomized 2:1 to receive body weight- adjusted doses of rivaroxaban for oral suspension or comparator (unfractionated heparin, low molecular weight heparin, fondaparinux or VKA).

Discontinuation due to bleeding events occurred in 6 (1.8 %) patients in the rivaroxaban for oral suspension group and 3 (1.9 %) patients in the comparator group.

Table 14 shows the number of patients experiencing bleeding events in the EINSTEIN Junior study. In female patients who had experienced menarche, ages 12 to <18 years of age, menorrhagia occurred in 23 (27 %) female patients in the rivaroxaban for oral suspension group and 5 (10 %) female patients in the comparator group.

Table 14: Bleeding Events in EINSTEIN Junior Study–Safety Analysis Set - Main Treatment Period*
Parameter | Rivaroxaban for Oral Suspension † N=329 n (%) | Comparator Group‡ N=162 n (%)
Major bleeding§ | 0 | 2 (1.2)
Clinically relevant non-major bleeding¶ | 10 (3) | 1 (0.6)
Trivial bleeding | 113 (34.3) | 44 (27.2)
Any bleeding | 119 (36.2) | 45 (27.8)
* These events occurred after randomization until 3 months of treatment (1 month for patients <2 years with central venous catheter-related VTE (CVC-VTE). Patients may have more than one event.
† Treatment schedule: body weight-adjusted doses of rivaroxaban for oral suspension; randomized 2:1 (rivaroxaban for oral suspension: Comparator).
‡ Unfractionated heparin (UFH), low molecular weight heparin (LMWH), fondaparinux or VKA.
§ Defined as clinically overt bleeding associated with a decrease in hemoglobin of ≥2 g/dL, a transfusion of ≥2 units of packed red blood cells or whole blood, bleeding at a critical site, or with a fatal outcome.
¶ Defined as clinically overt bleeding, which did not meet the criteria for major bleeding, but was associated with medical intervention, unscheduled contact with a physician, temporary cessation of treatment, discomfort for the patient, or impairment of activities of daily life.

Non-bleeding adverse reactions reported in ≥5 % of rivaroxaban for oral suspension -treated patients are shown in Table 15.

Table 15: Other Adverse Reactions* Reported in Rivaroxaban for Oral Suspension-Treated Patients by ≥5 % in EINSTEIN Junior Study

Adverse Reaction | Rivaroxaban for Oral Suspension N=329 n (%) | Comparator Group N=162 n (%)
Pain in extremity | 23 (7) | 7 (4.3)
Fatigue† | 23 (7) | 7 (4.3)
* Adverse reaction with Relative Risk >1.5 for rivaroxaban for oral suspension versus comparator.
† The following terms were combined: fatigue, asthenia.

A clinically relevant adverse reaction in rivaroxaban for oral suspension -treated patients was vomiting (10.6 % in the rivaroxaban for oral suspension group vs 8 % in the comparator group).

Thromboprophylaxis in Pediatric Patients with Congenital Heart Disease (CHD) after the Fontan Procedure:

The data below are based on Part B of the UNIVERSE study which was designed to evaluate the safety and efficacy of rivaroxaban for oral suspension for thromboprophylaxis in 98 children with CHD after the Fontan procedure who took at least one dose of study drug. Patients in Part B were randomized 2:1 to receive either body weight-adjusted doses of rivaroxaban for oral suspension or aspirin (approximately 5 mg/kg).

Discontinuation due to bleeding events occurred in 1 (1.6 %) patient in the rivaroxaban for oral suspension group and no patients in the aspirin group.

Table 16 shows the number of patients experiencing bleeding events in the UNIVERSE study.

Table 16: Bleeding Events in UNIVERSE Study - Safety Analysis Set - On Treatment Plus 2 Days
Parameter | Rivaroxaban for Oral Suspension [Treatment schedule: body weight-adjusted doses of rivaroxaban for oral suspension or aspirin (approximately 5 mg/kg); randomized 2:1 (Rivaroxaban for Oral Suspension:Aspirin).] N=64 n (%) | Aspirin N=34 n (%)
Major Bleeding [Defined as clinically overt bleeding associated with a decrease in hemoglobin of ≥2 g/dL, a transfusion of the equivalent of ≥2 units of packed red blood cells or whole blood, bleeding at a critical site, or with a fatal outcome.] | 1 (1.6) | 0
Epistaxis leading to transfusion | 1 (1.6) | 0
Clinically relevant non-major (CRNM) bleeding [Defined as clinically overt bleeding, which did not meet the criteria for major bleeding, but was associated with medical intervention, unscheduled contact with a physician, temporary cessation of treatment, discomfort for the patient, or impairment of activities of daily life.] | 4 (6.3) | 3 (8.8)
Trivial bleeding | 21 (32.8) | 12 (35.3)
Any bleeding | 23 (35.9) | 14 (41.2)

Non-bleeding adverse reactions reported in ≥5 % of rivaroxaban for oral suspension-treated patients are shown in Table 17.

Table 17: Other Adverse Reactions*Reported by ≥5 % of Rivaroxaban for Oral Suspension-Treated Patients in UNIVERSE Study (Part B)
Adverse Reaction | Rivaroxaban for Oral Suspension N=64 n (%) | Aspirin N=34 n (%)
Cough | 10 (15.6) | 3 (8.8)
Vomiting | 9 (14.1) | 3 (8.8)
Gastroenteritis† | 8 (12.5) | 1 (2.9)
Rash† | 6 (9.4) | 2 (5.9)
* Adverse reaction with Relative Risk >1.5 for rivaroxaban for oral suspension versus aspirin.
† The following terms were combined:
Gastroenteritis: gastroenteritis, gastroenteritis viral
Rash: rash, rash maculo-papular, viral rash

6.2 Postmarketing Experience

The following adverse reactions have been identified during post-approval use of rivaroxaban for oral suspension. Because these reactions are reported voluntarily from a population of uncertain size, it is not always possible to reliably estimate their frequency or establish a causal relationship to drug exposure.

Blood and Lymphatic System Disorders: agranulocytosis, thrombocytopenia

Hepatobiliary Disorders: jaundice, cholestasis, hepatitis (including hepatocellular injury)

Immune System Disorders: hypersensitivity, anaphylactic reaction, anaphylactic shock, angioedema

Nervous System Disorders: hemiparesis

Renal Disorders: Anticoagulant-related nephropathy

Respiratory, Thoracic and Mediastinal Disorders: Eosinophilic pneumonia

Skin and Subcutaneous Tissue Disorders: Stevens-Johnson syndrome, drug reaction with eosinophilia and systemic symptoms (DRESS)

Injury, poisoning and procedural complications: Atraumatic splenic rupture

7 DRUG INTERACTIONS

7.1 General Inhibition and Induction Properties

Rivaroxaban is a substrate of CYP3A4/5, CYP2J2, and the P-gp and ATP-binding cassette G2 (ABCG2) transporters. Combined P-gp and strong CYP3A inhibitors increase exposure to rivaroxaban and may increase the risk of bleeding. Combined P-gp and strong CYP3A inducers decrease exposure to rivaroxaban and may increase the risk of thromboembolic events.

7.2 Drugs that Inhibit Cytochrome P450 3A Enzymes and Drug Transport Systems

Interaction with Combined P-gp and Strong CYP3A Inhibitors

Avoid concomitant administration of rivaroxaban for oral suspension with known combined P-gp and strong CYP3A inhibitors (e.g., ketoconazole and ritonavir) [see Warnings and Precautions (5.6) and Clinical Pharmacology (12.3)].

Although clarithromycin is a combined P-gp and strong CYP3A inhibitor, pharmacokinetic data suggests that no precautions are necessary with concomitant administration with rivaroxaban for oral suspension as the change in exposure is unlikely to affect the bleeding risk [see Clinical Pharmacology (12.3)].

Interaction with Combined P-gp and Moderate CYP3A Inhibitors in Patients with Renal Impairment

Rivaroxaban for oral suspension should not be used in patients with CrCl 15 to <80 mL/min who are receiving concomitant combined P-gp and moderate CYP3A inhibitors (e.g., erythromycin) unless the potential benefit justifies the potential risk [see Warnings and Precautions (5.4) and Clinical Pharmacology (12.3)].

7.3 Drugs that Induce Cytochrome P450 3A Enzymes and Drug Transport Systems

Avoid concomitant use of rivaroxaban for oral suspension with drugs that are combined P-gp and strong CYP3A inducers (e.g., carbamazepine, phenytoin, rifampin, St. John's wort) [see Warnings and Precautions (5.6) and Clinical Pharmacology (12.3)].

7.4 Anticoagulants and NSAIDs/Aspirin

Coadministration of enoxaparin, warfarin, aspirin, clopidogrel and chronic NSAID use may increase the risk of bleeding [see Clinical Pharmacology (12.3)].

Avoid concurrent use of rivaroxaban for oral suspension with other anticoagulants due to increased bleeding risk unless benefit outweighs risk. Promptly evaluate any signs or symptoms of blood loss if patients are treated concomitantly with aspirin, other platelet aggregation inhibitors, or NSAIDs [see Warnings and Precautions (5.2)].

8 USE IN SPECIFIC POPULATIONS

8.1 Pregnancy

Risk Summary

The limited available data on rivaroxaban for oral suspension in pregnant women are insufficient to inform a drug- associated risk of adverse developmental outcomes. Use rivaroxaban for oral suspension with caution in pregnant patients because of the potential for pregnancy related hemorrhage and/or emergent delivery. The anticoagulant effect of rivaroxaban for oral suspension cannot be reliably monitored with standard laboratory testing. Consider the benefits and risks of rivaroxaban for oral suspension for the mother and possible risks to the fetus when prescribing rivaroxaban for oral suspension to a pregnant woman [see Warnings and Precautions (5.2, 5.7)].

Adverse outcomes in pregnancy occur regardless of the health of the mother or the use of medications. The estimated background risk of major birth defects and miscarriage for the indicated populations is unknown. In the U.S. general population, the estimated background risk of major birth defects and miscarriage in clinically recognized pregnancies is 2 to 4 % and 15 to 20 %, respectively.

Clinical Considerations

Disease-Associated Maternal and/or Embryo/Fetal Risk:

Pregnancy is a risk factor for venous thromboembolism and that risk is increased in women with inherited or acquired thrombophilias. Pregnant women with thromboembolic disease have an increased risk of maternal complications including pre-eclampsia. Maternal thromboembolic disease increases the risk for intrauterine growth restriction, placental abruption and early and late pregnancy loss.

Fetal/Neonatal Adverse Reactions:

Based on the pharmacologic activity of Factor Xa inhibitors and the potential to cross the placenta, bleeding may occur at any site in the fetus and/or neonate.

Labor or Delivery:

All patients receiving anticoagulants, including pregnant women, are at risk for bleeding and this risk may be increased during labor or delivery [see Warnings and Precautions (5.7)]. The risk of bleeding should be balanced with the risk of thrombotic events when considering the use of rivaroxaban for oral suspension in this setting.

Data

Human Data:

There are no adequate or well-controlled studies of rivaroxaban for oral suspension in pregnant women, and dosing for pregnant women has not been established. Post-marketing experience is currently insufficient to determine a rivaroxaban-associated risk for major birth defects or miscarriage. In an in vitro placenta perfusion model, unbound rivaroxaban was rapidly transferred across the human placenta.

Animal Data:

Rivaroxaban crosses the placenta in animals. Rivaroxaban increased fetal toxicity (increased resorptions, decreased number of live fetuses, and decreased fetal body weight) when pregnant rabbits were given oral doses of ≥10 mg/kg rivaroxaban during the period of organogenesis. This dose corresponds to about 4 times the human exposure of unbound drug, based on AUC comparisons at the highest recommended human dose of 20 mg/day. Fetal body weights decreased when pregnant rats were given oral doses of 120 mg/kg during the period of organogenesis. This dose corresponds to about 14 times the human exposure of unbound drug. In rats, peripartal maternal bleeding and maternal and fetal death occurred at the rivaroxaban dose of 40 mg/kg (about 6 times maximum human exposure of the unbound drug at the human dose of 20 mg/day).

8.2 Lactation

Risk Summary

Rivaroxaban has been detected in human milk. There are insufficient data to determine the effects of rivaroxaban on the breastfed child or on milk production. Rivaroxaban and/or its metabolites were present in the milk of rats. The developmental and health benefits of breastfeeding should be considered along with the mother's clinical need for rivaroxaban for oral suspension and any potential adverse effects on the breastfed infant from rivaroxaban for oral suspension or from the underlying maternal condition (see Data).

Data

Animal Data:

Following a single oral administration of 3 mg/kg of radioactive [^14C]-rivaroxaban to lactating rats between Day 8 to 10 postpartum, the concentration of total radioactivity was determined in milk samples collected up to 32 hours post-dose. The estimated amount of radioactivity excreted with milk within 32 hours after administration was 2.1 % of the maternal dose.

8.3 Females and Males of Reproductive Potential

Females of reproductive potential requiring anticoagulation should discuss pregnancy planning with their physician.

The risk of clinically significant uterine bleeding, potentially requiring gynecological surgical interventions, identified with oral anticoagulants including rivaroxaban for oral suspension should be assessed in females of reproductive potential and those with abnormal uterine bleeding.

8.4 Pediatric Use

The safety and effectiveness of rivaroxaban for oral suspension have been established in pediatric patients from birth to less than 18 years for the treatment of VTE and the reduction in risk of recurrent VTE. Use of rivaroxaban for oral suspension is supported in these age groups by evidence from adequate and well-controlled studies of rivaroxaban in adults with additional pharmacokinetic, safety and efficacy data from a multicenter, prospective, open-label, active-controlled randomized study in 500 pediatric patients from birth to less than 18 years of age. Rivaroxaban for oral suspension was not studied and therefore dosing cannot be reliably determined or recommended in children less than 6 months who were less than 37 weeks of gestation at birth; had less than 10 days of oral feeding, or had a body weight of less than 2.6 kg [see Dosage and Administration (2.2), Adverse Reactions (6.1), Clinical Pharmacology (12.3) and Clinical Studies (14.8).

The safety and effectiveness of rivaroxaban for oral suspension have been established for use in pediatric patients aged 2 years and older with congenital heart disease who have undergone the Fontan procedure. Use of rivaroxaban for oral suspension is supported in these age groups by evidence from adequate and well- controlled studies of rivaroxaban in adults with additional data from a multicenter, prospective, open-label, active controlled study in 112 pediatric patients to evaluate the single- and multiple-dose pharmacokinetic properties of rivaroxaban for oral suspension and the safety and efficacy of rivaroxaban for oral suspension when used for thromboprophylaxis for 12 months in children with single ventricle physiology who had the Fontan procedure [see Dosage and Administration (2.2), Adverse Reactions (6.1), Clinical Pharmacology (12.3) and Clinical Studies (14.9)].

Although not all adverse reactions identified in the adult population have been observed in clinical trials of children and adolescent patients, the same warnings and precautions for adults should be considered for children and adolescents.

8.5 Geriatric Use

Of the total number of adult patients in clinical trials for the approved indications of rivaroxaban (N=64,943 patients), 64 percent were 65 years and over, with 27 percent 75 years and over. In clinical trials the efficacy of rivaroxaban in the elderly (65 years or older) was similar to that seen in patients younger than 65 years. Both thrombotic and bleeding event rates were higher in these older patients [see Clinical Pharmacology (12.3) and Clinical Studies (14)].

8.6 Renal Impairment

In pharmacokinetic studies, compared to healthy adult subjects with normal creatinine clearance, rivaroxaban exposure increased by approximately 44 to 64 % in adult subjects with renal impairment. Increases in pharmacodynamic effects were also observed [see Clinical Pharmacology (12.3)].

Pediatric Use

No dosage adjustment is required in patients 1 year of age or older with mild renal impairment (eGFR 50 to ≤ 80 mL/min/1.73 m^2). There are limited clinical data in pediatric patients 1 year or older with moderate or severe renal impairment (eGFR <50 mL/min/1.73 m^2); therefore, avoid the use of rivaroxaban for oral suspension in these patients.

There are no clinical data in pediatric patients younger than 1 year with serum creatinine results above 97.5th percentile; therefore, avoid the use of rivaroxaban for oral suspension in these patients [see Dosage and Administration (2.2)].

8.7 Hepatic Impairment

In a pharmacokinetic study, compared to healthy adult subjects with normal liver function, AUC increases of 127 % were observed in adult subjects with moderate hepatic impairment (Child-Pugh B).

The safety or PK of rivaroxaban for oral suspension in patients with severe hepatic impairment (Child-Pugh C) has not been evaluated [see Clinical Pharmacology (12.3)].

Avoid the use of rivaroxaban for oral suspension in patients with moderate (Child-Pugh B) and severe (Child-Pugh C) hepatic impairment or with any hepatic disease associated with coagulopathy.

No clinical data are available in pediatric patients with hepatic impairment.

10 OVERDOSAGE

Overdose of rivaroxaban for oral suspension may lead to hemorrhage. Discontinue rivaroxaban for oral suspension and initiate appropriate therapy if bleeding complications associated with overdosage occur. Rivaroxaban systemic exposure is not further increased at single doses >50 mg due to limited absorption. The use of activated charcoal to reduce absorption in case of rivaroxaban for oral suspension overdose may be considered. Due to the high plasma protein binding, rivaroxaban is not dialyzable [see Warnings and Precautions (5.2) and Clinical Pharmacology (12.3)]. Partial reversal of laboratory anticoagulation parameters may be achieved with use of plasma products. An agent to reverse the anti-factor Xa activity of rivaroxaban is available.

11 DESCRIPTION

Rivaroxaban, a factor Xa (FXa) inhibitor, is the active ingredient in rivaroxaban for oral suspension with the chemical name 5-Chloro-N-({(5S)-2-oxo-3-[4-(3-oxo-4-morpholinyl) phenyl]-1, 3-oxazolidin-5-yl}methyl)-2-thiophenecarboxamide. The molecular formula of rivaroxaban is C19H18ClN3O5S and the molecular weight is 435.88. The structural formula is:

Rivaroxaban is a pure (S)-enantiomer. It is white to yellowish powder. Rivaroxaban is soluble in dimethylsulfoxide and practically insoluble in water.

Rivaroxaban for oral suspension is supplied as granules in bottles containing 155 mg of rivaroxaban (1 mg of rivaroxaban per mL after reconstitution). The inactive ingredients are: anhydrous citric acid, carboxymethylcellulose sodium, hydroxypropyl methyl cellulose, mannitol, microcrystalline cellulose, sodium benzoate, sucralose, tutti frutti flavor and xanthan gum.

12 CLINICAL PHARMACOLOGY

12.1 Mechanism of Action

Rivaroxaban is a selective inhibitor of FXa. It does not require a cofactor (such as Anti-thrombin III) for activity. Rivaroxaban inhibits free FXa and prothrombinase activity. Rivaroxaban has no direct effect on platelet aggregation, but indirectly inhibits platelet aggregation induced by thrombin. By inhibiting FXa, rivaroxaban decreases thrombin generation.

12.2 Pharmacodynamics

Rivaroxaban produces dose-dependent inhibition of FXa activity. Clotting tests, such as prothrombin time (PT), activated partial thromboplastin time (aPTT) and HepTest®, are also prolonged dose-dependently. In children treated with rivaroxaban, the correlation between anti-factor Xa to plasma concentrations is linear with a slope close to 1.

Monitoring for anticoagulation effect of rivaroxaban using anti-FXa activity or a clotting test is not recommended.

Specific Populations

Renal Impairment:

The relationship between systemic exposure and pharmacodynamic activity of rivaroxaban was altered in adult subjects with renal impairment relative to healthy control subjects [see Use in Specific Populations (8.6)].

Table 18: Percentage Increase in Rivaroxaban PK and PD Measures in Adult Subjects with Renal Impairment Relative to Healthy Subjects from Clinical Pharmacology Studies
Measure | Parameter | Creatinine Clearance (mL/min)
Measure | Parameter | 50 to 79 | 30 to 49 | 15 to 29 | ESRD (on dialysis)* | ESRD (post-dialysis)*
Exposure | AUC | 44 | 52 | 64 | 47 | 56
FXa Inhibition | AUEC | 50 | 86 | 100 | 49 | 33
PT Prolongation | AUEC | 33 | 116 | 144 | 112 | 158

*Separate stand-alone study.

PT = Prothrombin time; FXa = Coagulation factor Xa; AUC = Area under the plasma concentration-time curve; AUEC = Area under the effect-time curve

Hepatic Impairment:

Anti-Factor Xa activity was similar in adult subjects with normal hepatic function and in mild hepatic impairment (Child-Pugh A class). There is no clear understanding of the impact of hepatic impairment beyond this degree on the coagulation cascade and its relationship to efficacy and safety.

12.3 Pharmacokinetics

Absorption

The absolute bioavailability of rivaroxaban is dose-dependent. For the 2.5 mg and 10 mg dose, it is estimated to be 80 % to 100 % and is not affected by food. Rivaroxaban 2.5 mg and 10 mg tablets can be taken with or without food. Rivaroxaban 20 mg administered in the fasted state has an absolute bioavailability of approximately 66%. Coadministration of rivaroxaban with food increases the bioavailability of the 20 mg dose (mean AUC and Cmax increasing by 39 % and 76 % respectively with food). Rivaroxaban 15 mg and 20 mg tablets should be taken with food.

The maximum concentrations (Cmax) of rivaroxaban appear 2 to 4 hours after tablet intake. The pharmacokinetics of rivaroxaban were not affected by drugs altering gastric pH. Coadministration of rivaroxaban (30 mg single dose) with the H2-receptor antagonist ranitidine (150 mg twice daily), the antacid aluminum hydroxide/magnesium hydroxide (10 mL) or rivaroxaban (20 mg single dose) with the PPI omeprazole (40 mg once daily) did not show an effect on the bioavailability and exposure of rivaroxaban (see Figure 3).

Absorption of rivaroxaban is dependent on the site of drug release in the GI tract. A 29 % and 56 % decrease in AUC and Cmax compared to tablet was reported when rivaroxaban granulate is released in the proximal small intestine. Exposure is further reduced when drug is released in the distal small intestine, or ascending colon. Avoid administration of rivaroxaban distal to the stomach which can result in reduced absorption and related drug exposure.

In a study with 44 healthy subjects, both mean AUC and Cmax values for 20 mg rivaroxaban administered orally as a crushed tablet mixed in applesauce were comparable to that after the whole tablet. However, for the crushed tablet suspended in water and administered via an NG tube followed by a liquid meal, only mean AUC was comparable to that after the whole tablet, and Cmax was 18 % lower.

Distribution

Protein binding of rivaroxaban in human plasma is approximately 92 % to 95 %, with albumin being the main binding component. The steady-state volume of distribution in healthy subjects is approximately 50 L.

Metabolism

Approximately 51 % of an orally administered [^14C]-rivaroxaban dose was recovered as inactive metabolites in urine (30 %) and feces (21 %). Oxidative degradation catalyzed by CYP3A4/5 and CYP2J2 and hydrolysis are the major sites of biotransformation. Unchanged rivaroxaban was the predominant moiety in plasma with no major or active circulating metabolites.

Excretion

In a Phase 1 study, following the administration of [^14C]-rivaroxaban, approximately one-third (36 %) was recovered as unchanged drug in the urine and 7 % was recovered as unchanged drug in feces. Unchanged drug is excreted into urine, mainly via active tubular secretion and to a lesser extent via glomerular filtration (approximate 5:1 ratio). Rivaroxaban is a substrate of the efflux transporter proteins P-gp and ABCG2 (also abbreviated BCRP). Rivaroxaban's affinity for influx transporter proteins is unknown.

Rivaroxaban is a low-clearance drug, with a systemic clearance of approximately 10 L/hr in healthy volunteers following intravenous administration. The terminal elimination half-life of rivaroxaban is 5 to 9 hours in healthy subjects aged 20 to 45 years.

Specific Populations

The effects of level of renal impairment, age, body weight, and level of hepatic impairment on the pharmacokinetics of rivaroxaban are summarized in Figure 2.

Figure 2: Effect of Specific Adult Populations on the Pharmacokinetics of Rivaroxaban

Gender:

Gender did not influence the pharmacokinetics or pharmacodynamics of rivaroxaban for oral suspension.

Race:

Healthy Japanese subjects were found to have 20 to 40 % on average higher exposures compared to other ethnicities including Chinese. However, these differences in exposure are reduced when values are corrected for body weight.

Elderly:

The terminal elimination half-life is 11 to 13 hours in the elderly subjects aged 60 to 76 years [See Use in Specific Populations (8.5)].

Pediatric Patients:

The rate and extent of absorption were similar between the tablet and suspension. After repeated administration of rivaroxaban for the treatment of VTE, the Cmax of rivaroxaban in plasma was observed at median times of 1.5 to 2.2 hours in subjects who ranged from birth to less than 18 years of age.

In children who were 6 months to 9 years of age, in vitro plasma protein binding of rivaroxaban is approximately 90 %.

The half-life of rivaroxaban in plasma of pediatric patients treated for VTE decreased with decreasing age. Mean half-life values were 4.2 hours in adolescents, 3 hours in children 2 to 12 years of age, 1.9 hours in children 0.5 to <2 years of age, and 1.6 hours in children <0.5 years of age.

An exploratory analysis in pediatric patients treated for VTE did not reveal relevant differences in rivaroxaban exposure based on gender or race.

Renal Impairment:

The safety and pharmacokinetics of single-dose rivaroxaban (10 mg) were evaluated in a study in healthy subjects [CrCl ≥80 mL/min (n=8)] and in subjects with varying degrees of renal impairment (see Figure 2). Compared to healthy subjects with normal creatinine clearance, rivaroxaban exposure increased in subjects with renal impairment. Increases in pharmacodynamic effects were also observed [see Use in Specific Populations (8.6)].

Hemodialysis in ESRD Subjects:

Systemic exposure to rivaroxaban administered as a single 15 mg dose in ESRD subjects dosed 3 hours after the completion of a 4-hour hemodialysis session (post-dialysis) is 56 % higher when compared to subjects with normal renal function (see Table 18). The systemic exposure to rivaroxaban administered 2 hours prior to a 4-hour hemodialysis session with a dialysate flow rate of 600 mL/min and a blood flow rate in the range of 320 to 400 mL/min is 47 % higher compared to those with normal renal function. The extent of the increase is similar to the increase in patients with CrCl 15 to 50 mL/min taking rivaroxaban 15 mg. Hemodialysis had no significant impact on rivaroxaban exposure. Protein binding was similar (86 % to 89 %) in healthy controls and ESRD subjects in this study.

Pediatric Patients:

Limited clinical data are available in children 1 year or older with moderate or severe renal impairment (eGFR <50 mL/min/1.73 m^2) or in children younger than 1 year with serum creatinine results above 97.5th percentile [see Dosage and Administration (2.2) and Use in Specific Populations (8.6)].

Hepatic Impairment:

The safety and pharmacokinetics of single-dose rivaroxaban (10 mg) were evaluated in a study in healthy adult subjects (n=16) and adult subjects with varying degrees of hepatic impairment (see Figure 2). No patients with severe hepatic impairment (Child-Pugh C) were studied. Compared to healthy subjects with normal liver function, significant increases in rivaroxaban exposure were observed in subjects with moderate hepatic impairment (Child-Pugh B) (see Figure 2). Increases in pharmacodynamic effects were also observed [see Use in Specific Populations (8.7)].

No clinical data are available in pediatric patients with hepatic impairment.

Drug Interactions

In vitro studies indicate that rivaroxaban neither inhibits the major cytochrome P450 enzymes CYP1A2, 2C8, 2C9, 2C19, 2D6, 2J2, and 3A nor induces CYP1A2, 2B6, 2C19, or 3A. In vitro data also indicates a low rivaroxaban inhibitory potential for P-gp and ABCG2 transporters.

The effects of coadministered drugs on the pharmacokinetics of rivaroxaban exposure are summarized in Figure 3 [see Drug Interactions (7)].

Figure 3: Effect of Coadministered Drugs on the Pharmacokinetics of Rivaroxaban in Adults

Anticoagulants:

In a drug interaction study, single doses of enoxaparin (40 mg subcutaneous) and rivaroxaban (10 mg) given concomitantly resulted in an additive effect on anti-factor Xa activity. In another study, single doses of warfarin (15 mg) and rivaroxaban (5 mg) resulted in an additive effect on factor Xa inhibition and PT. Neither enoxaparin nor warfarin affected the pharmacokinetics of rivaroxaban (see Figure 3).

NSAIDs/Aspirin:

In a study for another indication, concomitant aspirin use (almost exclusively at a dose of 100 mg or less) during the double-blind phase was identified as an independent risk factor for major bleeding. NSAIDs are known to increase bleeding, and bleeding risk may be increased when NSAIDs are used concomitantly with rivaroxaban for oral suspension. Neither naproxen nor aspirin affected the pharmacokinetics of rivaroxaban (see Figure 3).

Clopidogrel:

In two drug interaction studies where clopidogrel (300 mg loading dose followed by 75 mg daily maintenance dose) and rivaroxaban (15 mg single dose) were coadministered in healthy subjects, an increase in bleeding time to 45 minutes was observed in approximately 45 % and 30 % of subjects in these studies, respectively. The change in bleeding time was approximately twice the maximum increase seen with either drug alone. There was no change in the pharmacokinetics of either drug.

Drug-Disease Interactions with Drugs that Inhibit Cytochrome P450 3A Enzymes and Drug Transport Systems:

In a pharmacokinetic trial, rivaroxaban tablets was administered as a single dose in subjects with mild (CrCl = 50 to 79 mL/min) or moderate renal impairment (CrCl = 30 to 49 mL/min) receiving multiple doses of erythromycin (a combined P-gp and moderate CYP3A inhibitor). Compared to rivaroxaban tablets administered alone in subjects with normal renal function (CrCl >80 mL/min), subjects with mild and moderate renal impairment concomitantly receiving erythromycin reported a 76 % and 99 % increase in AUCinf and a 56 % and 64 % increase in Cmax, respectively. Similar trends in pharmacodynamic effects were also observed.

12.6 QT/QTc Prolongation

In a thorough QT study in healthy men and women aged 50 years and older, no QTc prolonging effects were observed for rivaroxaban (15 mg and 45 mg, single-dose).

13 NONCLINICAL TOXICOLOGY

13.1 Carcinogenesis, Mutagenesis, Impairment of Fertility

Rivaroxaban was not carcinogenic when administered by oral gavage to mice or rats for up to 2 years. The systemic exposures (AUCs) of unbound rivaroxaban in male and female mice at the highest dose tested (60 mg/kg/day) were 1- and 2-times, respectively, the human exposure of unbound drug at the human dose of 20 mg/day. Systemic exposures of unbound drug in male and female rats at the highest dose tested (60 mg/kg/day) were 2- and 4-times, respectively, the human exposure.

Rivaroxaban was not mutagenic in bacteria (Ames-Test) or clastogenic in V79 Chinese hamster lung cells in vitro or in the mouse micronucleus test in vivo.

No impairment of fertility was observed in male or female rats when given up to 200 mg/kg/day of rivaroxaban orally. This dose resulted in exposure levels, based on the unbound AUC, at least 13 times the exposure in humans given 20 mg rivaroxaban daily.

14 CLINICAL STUDIES

14.8 Treatment of Venous Thromboembolism and Reduction in Risk of Recurrent Venous Thromboembolism in Pediatric Patients

Rivaroxaban for oral suspension for the treatment of venous thromboembolism (VTE) and reduction in the risk of recurrent VTE was evaluated in the EINSTEIN Junior Phase 3 study [NCT02234843], a multicenter, open-label, active-controlled, randomized study in 500 pediatric patients from birth to less than 18 years with confirmed VTE. There were 276 children aged 12 to <18 years, 101 children aged 6 to <12 years, 69 children aged 2 to <6 years, and 54 children aged <2 years. Patients <6 months of age were excluded from enrollment if they were <37 weeks of gestation at birth, or had <10 days of oral feeding, or had a body weight of <2.6 kg.

Index VTE was classified as either central venous catheter-related VTE (CVC-VTE), cerebral vein and sinus thrombosis (CVST), and all other VTE including DVT and PE (non-CVC-VTE).

Patients received initial treatment with therapeutic dosages of unfractionated heparin (UFH), low molecular weight heparin (LMWH), or fondaparinux for at least 5 days, and were randomized 2:1 to receive either body weight-adjusted doses of rivaroxaban for oral suspension (exposures to match that of 20 mg daily dose in adults) or comparator group (UFH, LMWH, fondaparinux or VKA) for a main study treatment period of 3 months (or 1 month for children <2 years with CVC-VTE). A diagnostic imaging test was obtained at baseline and at the end of the main study treatment. When clinically necessary, treatment was extended up to 12 months in total (or up to 3 months in total for children <2 years with CVC-VTE).

Table 28 displays the primary and secondary efficacy results.

Table 28: Efficacy Results in EINSTEIN Junior Study – Full Analysis Set
Event | Rivaroxaban for Oral Suspension * N=335 n (%) (95 % CI)† | Comparator Group‡ N=165 n (%) (95 % CI)† | Rivaroxaban for Oral Suspension vs. Comparator Group Risk Difference (95 % CI)§ | Rivaroxaban for Oral Suspension vs. Comparator Group Hazard Ratio (95 % CI)
Primary efficacy | 4 (1.2) | 5 (3) | -1.8 % | 0.4
outcome: | 4 (1.2) | 5 (3) | -1.8 % | 0.4
Symptomatic | (0.4 %, 3 %) | (1.2 %, 6.6 %) | (-6 %, 0.6 %) | (0.11, 1.41)
recurrent VTE | (0.4 %, 3 %) | (1.2 %, 6.6 %) | (-6 %, 0.6 %) | (0.11, 1.41)
Secondary efficacy outcome: Symptomatic recurrent VTE or asymptomatic deterioration on repeat imaging | 5 (1.5) (0.6 %, 3.4 %) | 6 (3.6) (1.6 %, 7.6 %) | -2.1 % (-6.5 %, 0.6 %)
* Treatment schedule: body weight-adjusted doses of rivaroxaban for oral suspension (exposures to match that of 20 mg daily dose in adults); randomized 2:1 (Rivaroxaban for oral suspension: Comparator).
† Confidence intervals for incidence proportion were calculated by applying the method of Blyth-Still-Casella.
‡ Unfractionated heparin (UFH), low molecular weight heparin (LMWH), fondaparinux or VKA.
§ Confidence intervals for difference in incidence proportions were calculated by unstratified exact method according to Agresti-Min using the standardized test statistic and inverting a two-sided test.

Complete resolution of thrombus on repeat imaging without recurrent VTE occurred in 128 of 335 children (38.2 %, 95 % CI 33 %, 43.5 %) in the rivaroxaban for oral suspension group and 43 of 165 children (26.1 %, 95 % CI 19.8 %, 33 %) in the comparator group. Symptomatic recurrent VTE or major bleeding events occurred in 4 of 335 children (1.2 %, 95 % CI 0.4 %, 3 %) in the rivaroxaban for oral suspension group and 7 of 165 children (4.2 %, 95 % CI 2 %, 8.4 %) in the comparator group.

14.9 Thromboprophylaxis in Pediatric Patients with Congenital Heart Disease after the Fontan Procedure

The efficacy and safety of rivaroxaban for oral suspension for thromboprophylaxis in pediatric patients with congenital heart disease who have undergone the Fontan procedure was evaluated in the UNIVERSE Phase 3 study [NCT02846532]. UNIVERSE was a prospective, open-label, active controlled, multicenter, 2-part study, designed to evaluate the single- and multiple-dose pharmacokinetic properties of rivaroxaban for oral suspension (Part A), and to evaluate the safety and efficacy of rivaroxaban for oral suspension when used for thromboprophylaxis for 12 months compared with aspirin (Part B) in children 2 to 8 years of age with single ventricle physiology who had the Fontan procedure. Patients in Part B were randomized 2:1 to receive either body weight-adjusted doses of rivaroxaban for oral suspension (exposures to match that of 10 mg daily dose in adults) or aspirin (approximately 5 mg/kg). Patients with eGFR <30 mL/min/1.73 m^2 were excluded.

The median time between Fontan procedure and the first dose of rivaroxaban for oral suspension was 4 (range: 2 to 61) days in Part A and 34 (range: 2 to 124) days in part B. In comparison, the median time to initiating aspirin was 24 (range 2 to 117) days.

Table 29 displays the primary efficacy results.

Table 29: Efficacy Results in UNIVERSE Study – Full Analysis Set
 | Part A* |  | Part B†
Event | Rivaroxaban for Oral Suspension N=12 n (%) (95 %CI)‡ | Rivaroxaban for Oral Suspension§ N=64 n (%) (95 % CI)‡ | Aspirin§ N=34 n (%) (95 % CI)‡ | Rivaroxaban for Oral Suspension vs. Aspirin Risk Difference (95 % CI)¶
Primary efficacy outcome: any thrombotic event | 1 (8.3) (0.4 %, 34.9 %) | 1 (1.6) (0.1 %, 7.8 %) | 3 (8.8) (2.4 %, 22.2 %) | -7.3 % (-21.7 %, 1.1 %)
Ischemic stroke | 0 (0 %, 23.6 %) | 0 (0 %, 5.6 %) | 1 (2.9) 0.2 %, 15.1 %) | -2.9 % (-16.2 %, 2.9 %)
Pulmonary embolism | 0 (0 %, 23.6 %) | 1 (1.6) (0.1 %, 7.8 %) | 0 (0 %, 9 %) | 1.6 % (-9.9 %, 8.4 %)
Venous thrombosis | 1 (8.3) (0.4 %, 34.9 %) | 0 (0 %, 5.6 %) | 2 (5.9) (1.1 %, 18.8 %) | -5.9 % (-20.6 %, -0.1 %)
* Part A: single arm; not randomized
† Part B: randomized 2:1 (Rivaroxaban for oral suspension: Aspirin)
‡ Confidence intervals for incidence proportion were calculated by applying the method of Blyth-Still-Casella.
§ Treatment schedule: body weight-adjusted doses of rivaroxaban (exposures to match that of 10 mg daily dose in adults) or aspirin (approximately 5 mg/kg)
¶ Confidence intervals for difference in incidence proportions were calculated by unstratified exact method according to Agresti-Min using the standardized test statistic and inverting a two-sided test.

16 HOW SUPPLIED/STORAGE AND HANDLING

Rivaroxaban for oral suspension is available in the strength and package listed below:

NDC 70748-355-01 Supplied as white to off-white granules in translucent HDPE bottle containing 155 mg rivaroxaban packaged with two oral dosing syringes. After reconstitution with 150 mL of purified water, 1 mL of the suspension contains 1 mg rivaroxaban.

Discard reconstituted suspension after "Discard after" date written on the bottle.

Storage of granules and reconstituted suspension:

Store at room temperature between 20°C and 25°C (68°F and 77°F); excursions permitted between 15°C and 30°C (59°F and 86°F) [see USP Controlled Room Temperature].

Do not freeze the granules or reconstituted suspension.

Keep out of the reach of children.

17 PATIENT COUNSELING INFORMATION

For the suspension, advise the patient and/or caregiver to read the FDA-approved patient labeling (Medication Guide and Instructions for Use).

Instructions for Patient Use

- Advise patients to take rivaroxaban for oral suspension only as directed.
- Remind patients to not discontinue rivaroxaban for oral suspension without first talking to their healthcare professional.

Pediatric Patients:

- The adult caregiver should administer the dose. Advise caregivers to use the syringes provided in the original carton.
- Advise the caregiver whether the dose needs to be taken with food or not [see Dosage and Administration (2.2)].
- If a child vomits or spits up the dose within 30 minutes after receiving the dose, a new dose should be given. However, if the child vomits more than 30 minutes after the dose is taken, the dose should not be re-administered and the next dose should be taken as scheduled. If a child vomits or spits up the dose repeatedly, the caregiver should contact the child's doctor right away [see Dosage and Administration (2.2)].
- For children who are unable to swallow whole tablets, rivaroxaban for oral suspension may be used.
- If a dose is missed, advise the patient according to the instructions in the Full Prescribing Information based on their dosing schedule [see Dosage and Administration (2.5)].

Bleeding Risks

- Advise patients to report any unusual bleeding or bruising to their physician. Inform patients that it might take them longer than usual to stop bleeding, and that they may bruise and/or bleed more easily when they are treated with rivaroxaban for oral suspension [see Warnings and Precautions (5.2)].
- If patients have had neuraxial anesthesia or spinal puncture, and particularly, if they are taking concomitant NSAIDs or platelet inhibitors, advise patients to watch for signs and symptoms of spinal or epidural hematoma, such as back pain, tingling, numbness (especially in the lower limbs), muscle weakness, and stool or urine incontinence. If any of these symptoms occur, advise the patient to contact his or her physician immediately [see Boxed Warning].

Invasive or Surgical Procedures

Instruct patients to inform their healthcare professional that they are taking rivaroxaban for oral suspension before any invasive procedure (including dental procedures) is scheduled.

Concomitant Medication and Herbals

Advise patients to inform their physicians and dentists if they are taking, or plan to take, any prescription or over-the-counter drugs or herbals, so their healthcare professionals can evaluate potential interactions [see Drug Interactions (7)].

Pregnancy and Pregnancy-Related Hemorrhage

- Advise patients to inform their physician immediately if they become pregnant or intend to become pregnant during treatment with rivaroxaban for oral suspension [see Use in Specific Populations (8.1)].
- Advise pregnant women receiving rivaroxaban for oral suspension to immediately report to their physician any bleeding or symptoms of blood loss [see Warnings and Precautions (5.7)].

Lactation

Advise patients to discuss with their physician the benefits and risks of rivaroxaban for oral suspension for the mother and for the child if they are nursing or intend to nurse during anticoagulant treatment [see Use in Specific Populations (8.2)].

Females and Males of Reproductive Potential

Advise patients who can become pregnant to discuss pregnancy planning with their physician [see Use in Specific Populations (8.3)].

LUPIN and the are registered trademarks of Lupin Pharmaceuticals, Inc.

Manufactured for:

Lupin Pharmaceuticals, Inc.

Naples, FL 34108,

United States

Manufactured by:

Lupin Limited

Chhatrapati Sambhajinagar - 431 210

India

Revised: July 2025

MEDICATION GUIDE
Rivaroxaban (RIV-a-ROX-a-ban) for Oral Suspension

What is the most important information I should know about rivaroxaban for oral suspension?
Rivaroxaban for oral suspension may cause serious side effects, including:

- Increased risk of blood clots if you stop taking rivaroxaban for oral suspension . People with atrial fibrillation (a type of irregular heart beat) that is not caused by a heart valve problem (non-valvular) are at an increased risk of forming a blood clot in the heart, which can travel to the brain, causing a stroke, or to other parts of the body. Rivaroxaban for oral suspension lowers your chance of having a stroke by helping to prevent clots from forming. If you stop taking rivaroxaban for oral suspension, you may have increased risk of forming a clot in your blood.

Do not stop taking rivaroxaban for oral suspension without talking to the doctor who prescribes it for you. Stopping rivaroxaban for oral suspension increases your risk of having a stroke . If you have to stop taking rivaroxaban for oral suspension, your doctor may prescribe another blood thinner medicine to prevent a blood clot from forming.

- Increased risk of bleeding. Rivaroxaban for oral suspension can cause bleeding which can be serious and may lead to death. This is because rivaroxaban for oral suspension is a blood thinner medicine (anticoagulant) that lowers blood clotting. During treatment with rivaroxaban for oral suspension you are likely to bruise more easily, and it may take longer for bleeding to stop. You may have a higher risk of bleeding if you take rivaroxaban for oral suspension and have certain other medical problems.

You may have a higher risk of bleeding if you take rivaroxaban for oral suspension and take other medicines that increase your risk of bleeding, including:
○ aspirin or aspirin containing products
○ long-term (chronic) use of non-steroidal anti-inflammatory drugs (NSAIDs)
○ warfarin sodium (Coumadin®, Jantoven®)
○ any medicine that contains heparin
○ clopidogrel (Plavix®)
○ selective serotonin reuptake inhibitors (SSRIs) or serotonin norepinephrine reuptake inhibitors (SNRIs)
○ other medicines to prevent or treat blood clots
Tell your doctor if you take any of these medicines. Ask your doctor or pharmacist if you are not sure if your medicine is one listed above.
Call your doctor or get medical help right away if you or your child develop any of these signs or symptoms of bleeding:
○ unexpected bleeding or bleeding that lasts a long time, such as:
▪ nose bleeds that happen often
▪ unusual bleeding from the gums
▪ menstrual bleeding that is heavier than normal or vaginal bleeding
○ bleeding that is severe or you cannot control
○ red, pink or brown urine
○ bright red or black stools (looks like tar)
○ cough up blood or blood clots
○ vomit blood or your vomit looks like "coffee grounds"
○ headaches, feeling dizzy or weak
○ pain, swelling, or new drainage at wound sites
○ left upper belly (abdominal) pain, pain below the left rib cage or at the tip of your left shoulder or diffuse abdominal discomfort (these may be symptoms of rupture of the spleen)

- Spinal or epidural blood clots (hematoma). People who take a blood thinner medicine (anticoagulant) like rivaroxaban for oral suspension, and have medicine injected into their spinal and epidural area, or have a spinal puncture have a risk of forming a blood clot that can cause long-term or permanent loss of the ability to move (paralysis). Your risk of developing a spinal or epidural blood clot is higher if:
  - a thin tube called an epidural catheter is placed in your back to give you certain medicine
  - you take NSAIDs or a medicine to prevent blood from clotting
  - you have a history of difficult or repeated epidural or spinal punctures
  - you have a history of problems with your spine or have had surgery on your spine

If you take rivaroxaban for oral suspension and receive spinal anesthesia or have a spinal puncture, your doctor should watch you closely for symptoms of spinal or epidural blood clots.
Tell your doctor right away if you have:

- back pain
- muscle weakness (especially in your legs and feet)
- tingling
- loss of control of the bowels or bladder (incontinence)
- numbness

Rivaroxaban for oral suspension is not for use in people with artificial heart valves.
Rivaroxaban for oral suspension is not for use in people with antiphospholipid syndrome (APS), especially with positive triple antibody testing.

What is rivaroxaban for oral suspension?
Rivaroxaban for oral suspension is used in children to:
treat blood clots or reduce the risk of blood clots from happening again in children from birth to less than 18 years, after receiving at least 5 days of treatment with injectable or intravenous medicines used to treat blood clots.
help prevent blood clots in children 2 years and older with congenital heart disease after the Fontan procedure.
Rivaroxaban for oral suspension was not studied and is not recommended in children less than 6 months of age who:
were less than 37 weeks of growth (gestation) at birth
had less than 10 days of oral feeding, or
had a body weight of less than 5.7 pounds (2.6 kg)

Do not take rivaroxaban for oral suspension if you or your child:
currently have certain types of abnormal bleeding. Talk to your doctor before taking rivaroxaban for oral suspension if you currently have unusual bleeding.
are allergic to rivaroxaban or any of the ingredients in rivaroxaban for oral suspension. See the end of this Medication Guide for a complete list of ingredients in rivaroxaban for oral suspension.

Before taking rivaroxaban for oral suspension, tell your doctor about all of your medical conditions, including if you or your child:
have or ever had bleeding problems
have liver or kidney problems
have antiphospholipid syndrome (APS)
are pregnant or plan to become pregnant. It is not known if rivaroxaban for oral suspension will harm your unborn baby.
o Tell your doctor right away if you become pregnant during treatment with rivaroxaban for oral suspension. Taking rivaroxaban for oral suspension while you are pregnant may increase the risk of bleeding in you or in your unborn baby.
o Females who are able to become pregnant: Talk with your doctor about pregnancy planning during treatment with rivaroxaban for oral suspension. Talk with your doctor about your risk for severe uterine bleeding if you are treated with blood thinner medicines, including rivaroxaban for oral suspension.
o If you take rivaroxaban for oral suspension during pregnancy tell your doctor right away if you have any signs or symptoms of bleeding or blood loss. See "What is the most important information I should know about rivaroxaban for oral suspension?" for signs and symptoms of bleeding.

- are breastfeeding or plan to breastfeed. Rivaroxaban can pass into your breast milk. Talk to your doctor about the best way to feed your baby during treatment with rivaroxaban for oral suspension.

Tell all of your doctors and dentists that you or your child are taking rivaroxaban for oral suspension. They should talk to the doctor who prescribed rivaroxaban for oral suspension for you before you have any surgery, medical or dental procedure.
Tell your doctor about all the medicines you or your child take, including prescription and over-the-counter medicines, vitamins, and herbal supplements.
Some of your other medicines may affect the way rivaroxaban for oral suspension works, causing side effects. Certain medicines may increase your risk of bleeding. See "What is the most important information I should know about rivaroxaban for oral suspension?"
Especially tell your doctor if you or your child take:

- ketoconazole
- erythromycin
- phenytoin
- st. John's wort
- ritonavir
- carbamazepine
- rifampin

How should I take rivaroxaban for oral suspension?
• Take rivaroxaban for oral suspension exactly as prescribed by your doctor.
• Do not change your dose or stop taking rivaroxaban for oral suspension unless your doctor tells you to. Your doctor may change your dose if needed.
• Your doctor will decide how long you should take rivaroxaban for oral suspension.
• Rivaroxaban for oral suspension may need to be stopped for one or more days before any surgery or medical or dental procedure. Your doctor will tell you when to stop taking rivaroxaban for oral suspension and when to start taking rivaroxaban for oral suspension again after your surgery or procedure.
• If you need to stop taking rivaroxaban for oral suspension for any reason, talk to the doctor who prescribed rivaroxaban for oral suspension to you to find out when you should stop taking it. Do not stop taking rivaroxaban for oral suspension without first talking to the doctor who prescribes it to you.
• Do not run out of rivaroxaban for oral suspension. Refill your prescription of rivaroxaban for oral suspension before you run out. When leaving the hospital following a hip or knee replacement, be sure that you will have rivaroxaban for oral suspension available to avoid missing any doses.
• If you take too much rivaroxaban for oral suspension, go to the nearest hospital emergency room or call your doctor right away.
For children who take rivaroxaban for oral suspension:
o The dose of rivaroxaban for oral suspension depends on your child's body weight and will be calculated by your child's doctor. Your child's doctor will tell you if rivaroxaban for oral suspension can be given to your child with or without food.
o The adult caregiver should give the dose.
o If your child is taking the oral suspension, use the syringes provided in the original carton. The suspension will be prepared by the pharmacy. See the Instructions for Use included in the carton on how to properly give a dose of rivaroxaban for oral suspension to your child.
o Do not switch between the rivaroxaban for oral suspension or tablet without first talking to your doctor.
o If your child vomits or spits up:

- right after or within 30 minutes of taking the oral suspension, give a new full dose.
- more than 30 minutes after taking the oral suspension, do not give the dose again. Give the next dose at the regularly scheduled time.
- if vomiting or spitting up persists, contact your child's doctor right away.

o If your child misses a dose:

- If your child is taking rivaroxaban for oral suspension 1 time a day, give the dose as soon as you remember on the same day. If this is not possible, skip this dose and give the next dose at the regularly scheduled time.
- If your child is taking rivaroxaban for oral suspension 2 times a day, give the missed morning dose as soon as you remember. You may give the missed morning dose together with the evening dose. However, a missed evening dose can only be taken in the same evening.
- If your child is taking rivaroxaban for oral suspension 3 times a day, skip the missed dose and give the next dose at the regularly scheduled time.

What are the possible side effects of rivaroxaban for oral suspension?
Rivaroxaban for oral suspension may cause serious side effects:

- See "What is the most important information I should know about rivaroxaban for oral suspension?"

The most common side effects of rivaroxaban for oral suspension in children include:

- Bleeding
- Cough
- Vomiting
- inflamed stomach and gut

Call your doctor for medical advice about side effects. You may report side effects to FDA at 1800-FDA-1088. You may also report side effect to Lupin Pharmaceuticals, Inc. at 1-800-399-2561 or visit www.lupin.com.

How should I store rivaroxaban for oral suspension?

- Store rivaroxaban for oral suspension at room temperature between 68°F to 77°F (20°C to 25°C).
- Store syringes and bottle upright in the original carton for rivaroxaban for oral suspension.
- Do not freeze rivaroxaban for oral suspension.

Keep rivaroxaban for oral suspension and all medicines out of the reach of children.
Discard rivaroxaban for oral suspension after "Discard after" date written on the bottle.

General information about the safe and effective use of rivaroxaban for oral suspension.
Medicines are sometimes prescribed for purposes other than those listed in a Medication Guide. Do not use rivaroxaban for oral suspension for a condition for which it was not prescribed. Do not give rivaroxaban for oral suspension to other people, even if they have the same symptoms that you have. It may harm them. You can ask your pharmacist or doctor for information about rivaroxaban for oral suspension that is written for health professionals.

What are the ingredients in rivaroxaban for oral suspension?
Active ingredient: rivaroxaban
Inactive ingredients:
anhydrous citric acid, carboxymethylcellulose sodium, hydroxypropyl methyl cellulose, mannitol, microcrystalline cellulose, sodium benzoate, sucralose, tutti frutti flavor and xanthan gum.

This Medication Guide has been approved by the U.S. Food and Drug Administration

The brands listed are trademarks of their respective owners and are not trademarks of Lupin Pharmaceuticals, Inc. The makers of these brands are not affiliated with and do not endorse Lupin Pharmaceuticals, Inc. or its products.

LUPIN and the are registered trademarks of Lupin Pharmaceuticals, Inc.

Manufactured for:

Lupin Pharmaceuticals, Inc.

Naples, FL 34108,

United States

Manufactured by:

Lupin Limited

Chhatrapati Sambhajinagar - 431 210

India

Revised: July 2025 ID#: 280951

INSTRUCTIONS FOR USE

Rivaroxaban (RIV-a-ROX-a-ban) for Oral Suspension

This Instructions for Use contains information on how to give a dose of rivaroxaban for oral suspension.

Read this Instructions for Use before giving rivaroxaban for oral suspension and each time you get a refill. There may be new information. This leaflet does not take the place of talking with your doctor about your child's medical condition or treatment.

Important information:

- Rivaroxaban for oral suspension is for oral use only.
- Give rivaroxaban for oral suspension to your child exactly as prescribed by your doctor. The adult caregiver should give the dose. If you have questions, contact your doctor or pharmacist for more information on giving a dose.
- Only use the oral dosing syringe provided with rivaroxaban for oral suspension.Contact your doctor or pharmacist if the oral dosing syringe is missing, lost or damaged.

Storage Information:

Store rivaroxaban for oral suspension at room temperature between 68°F to 77°F (20°C to 25°C). Do not freeze.

Store the bottle upright with the oral dosing syringes in the original carton.

Keep rivaroxaban for oral suspension and all medicines out of reach of children.

Rivaroxaban for Oral Suspension Oral Dosing Syringe:

Rivaroxaban for Oral Suspension Bottle

Step 1: | Get Ready

Check "Discard after" date on the rivaroxaban for oral suspension bottle.

If "Discard after" date has passed, do not use and call your doctor or pharmacist

Wash hands.

Wash your hands well with soap and warm water.

Step 2: | Prepare Rivaroxaban for Oral Suspension

Check rivaroxaban for oral suspension.

If there are lumps or granules at the bottom of the bottle, shake the bottle slowly again for 10 seconds.

Step 3: | Check the prescribed dose

Find your dose line.

You can use either side of the syringe to set your dose.

If using mL side of syringe:

Top of the plunger should line up with the prescribed mL.

If using color side of syringe:

Top of the plunger should line up with the prescribed mL dose line at the bottom of the color band.

Only use the oral dosing syringe provided with rivaroxaban for oral suspension.

If your dose is more than 5 mL.

You will need to use the same syringe more than one time. Repeat Steps 4 and 5 to complete your dose. Ask your pharmacist if you are not sure.

Step 4: | Set prescribed dose

Push plunger all the way in to remove air.

Insert oral dosing syringe into bottle adaptor.

Twist off the cap from the bottle.

Do not remove the bottle adaptor from the bottle Insert the syringe tip into the bottle adaptor.

Fill oral dosing syringe.

Turn the bottle upside down, as shown.

Pull the plunger to fill the oral dosing syringe slightly past your prescribed dose line to help remove any air bubbles.

Tap syringe to move air bubbles to the top.

Doing this helps set the correct dose.

Adjust to your prescribed dose.

If using mL side of syringe: Push plunger to align with the prescribed dose line.

If using color side of syringe: Push plunger to align with the prescribed mL dose line at the bottom of the color band.

Remove oral dosing syringe.

Place the bottle on a flat surface.

Remove the oral dosing syringe from the bottle.

Step 5: | Give the dose

Give the dose.

Place the oral dosing syringe gently into the child's mouth with the tip of the syringe pointing toward the cheek and slowly press the plunger.

This allows the child to swallow naturally.

Make sure the child swallows the full dose.

If your child vomits or spits out the medicine repeatedly, contact your child's doctor right away.

If your dose is more than 5 mL , you will need to use the same syringe more than one time. Repeat Steps 4 and 5 to complete your dose

Step 6: | Rinse and store

Close rivaroxaban for oral suspension bottle and rinse oral dosing syringe.

Rinse the oral dosing syringe with tap water and let it air dry.

Disposing rivaroxaban for oral suspension bottle and syringe

- Throw the rivaroxaban for oral suspension bottle away in your household trash.
- Throw away any used oral dosing syringe with the opening of a new rivaroxaban for oral suspension bottle.
- Do not pour rivaroxaban for oral suspension down the drain(for example: sink, toilet, shower or tub)
- Do notrecycle the bottle

This Instructions for Use has been approved by the U.S. Food and Drug Administration.

LUPIN and the are registered trademarks of Lupin Pharmaceuticals, Inc.

Manufactured for:

Lupin Pharmaceuticals, Inc.

Naples, FL 34108,

United States

Manufactured by:

Lupin Limited

Chhatrapati Sambhajinagar - 431 210

India

Revised: July 2025 ID#: 280976

PACKAGE LABEL.PRINCIPAL DISPLAY PANEL

Rivaroxaban for Oral Suspension

1 mg/mL

(when reconstituted)

Container Label

NDC 70748-355-01

ATTENTION: Dispense the enclosed Medication Guide to each patient.

For Oral Use Only

image

Rivaroxaban for Oral Suspension

1 mg/mL

(when reconstituted)

Carton containing 1 bottle

NDC 70748-355-01

Pharmacist:

Must reconstitute before

dispensing.

Counsel caregiver on proper use.

ATTENTION: Dispense the enclosed Medication Guide to each patient.

For Oral Use Only

image